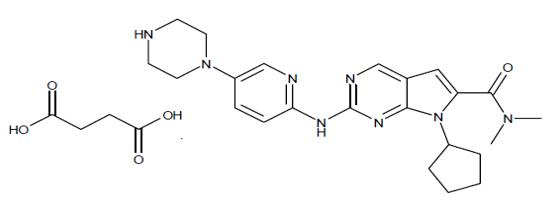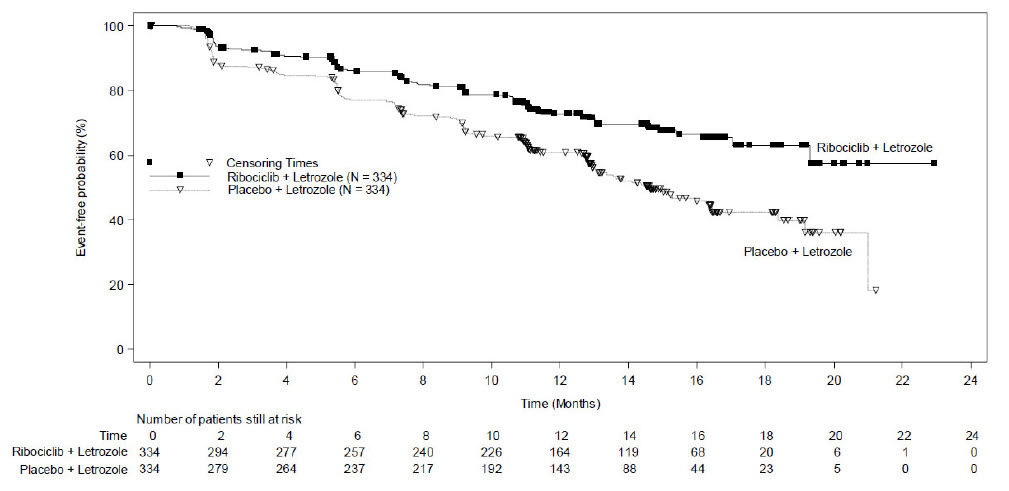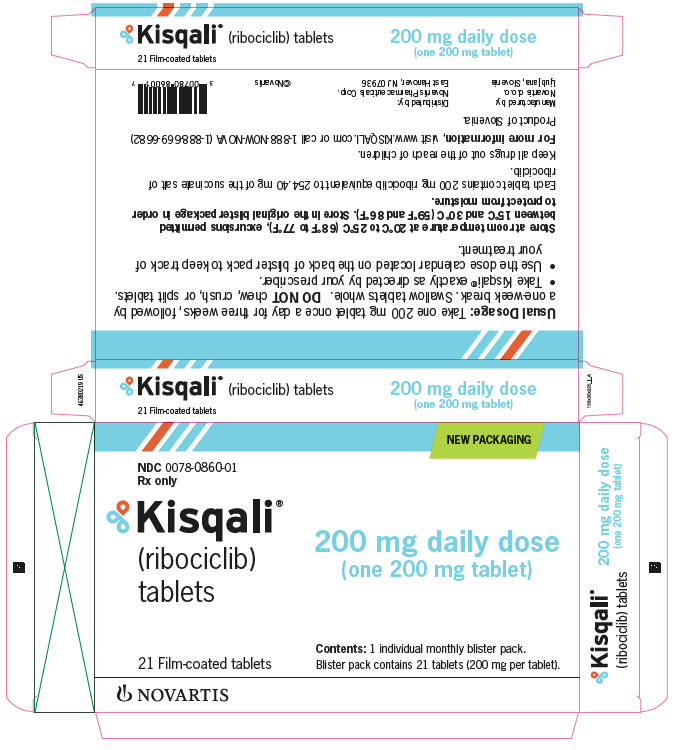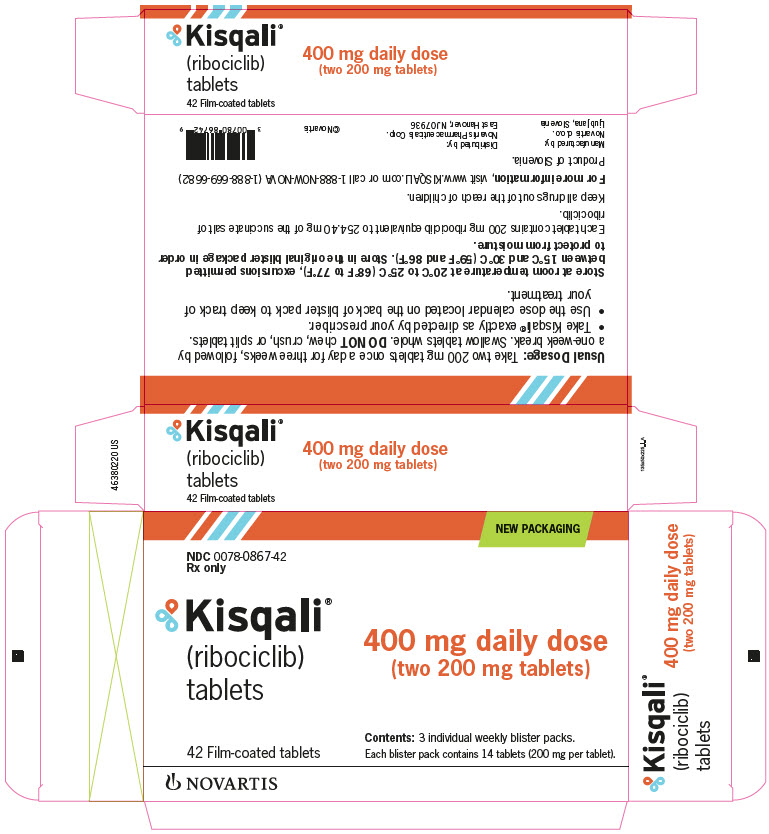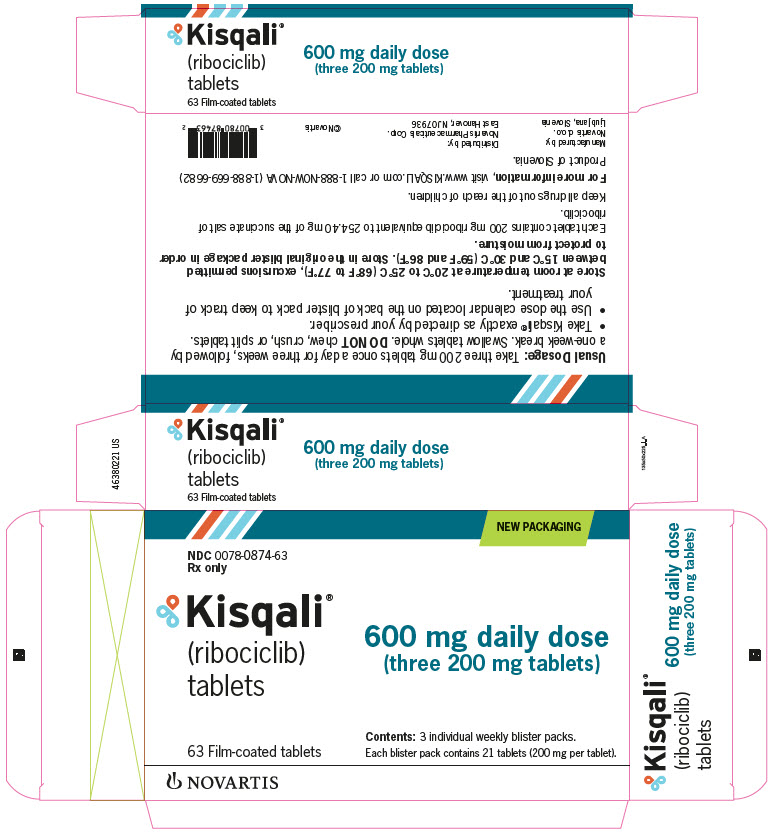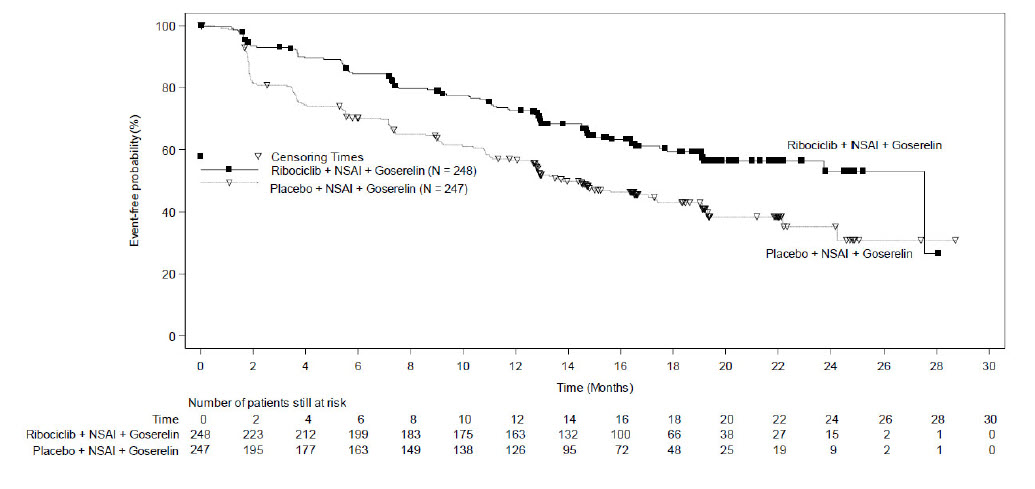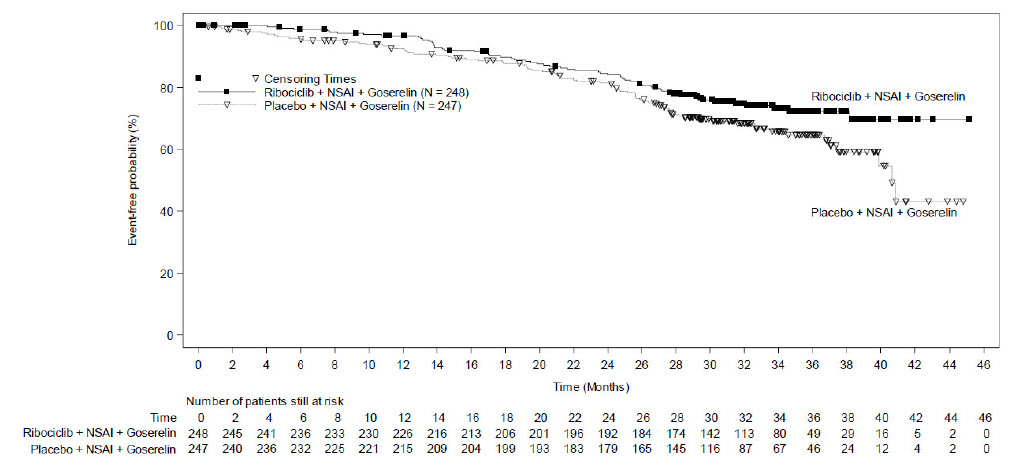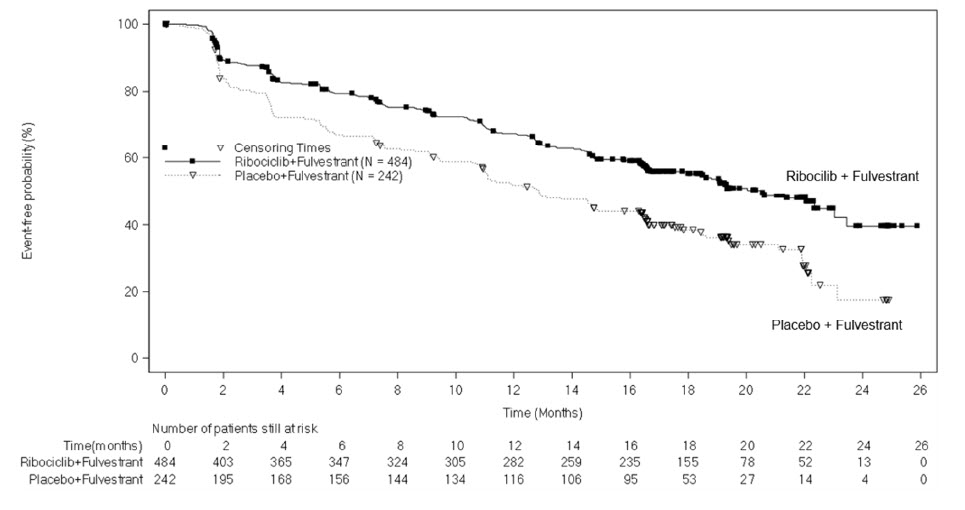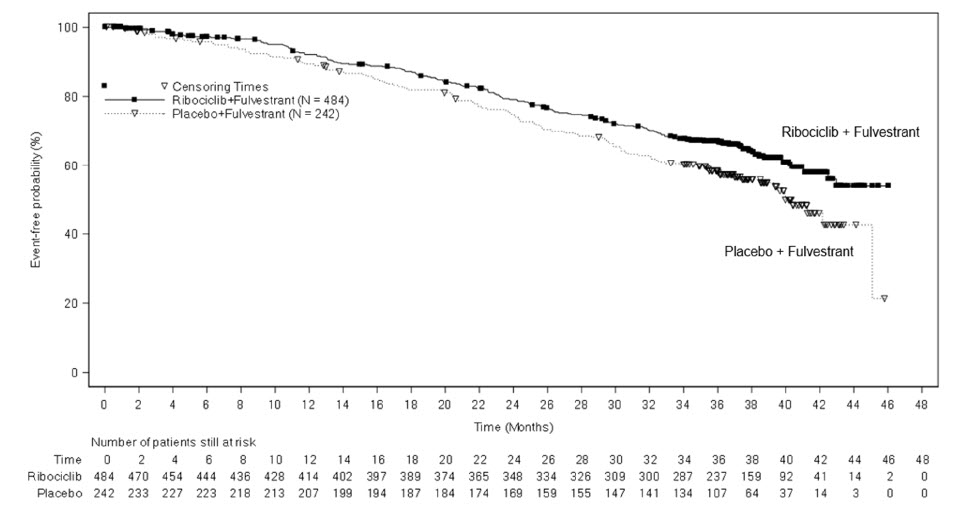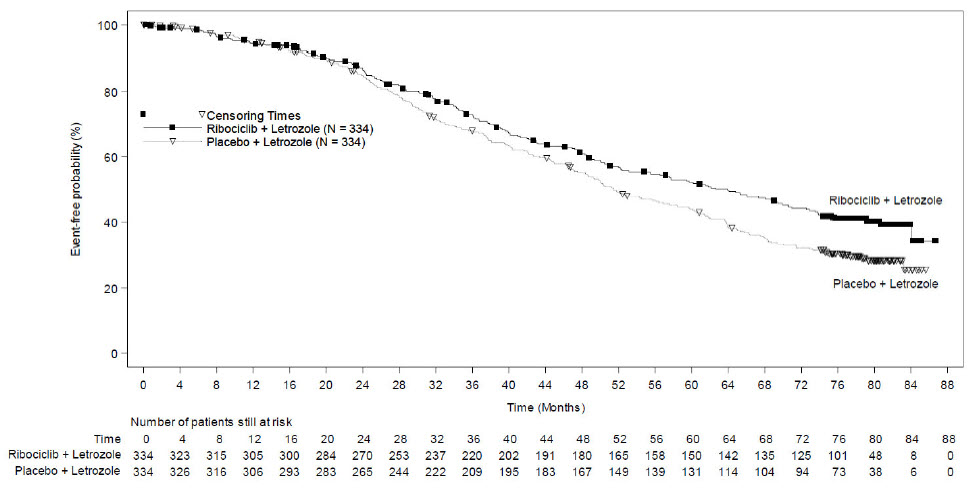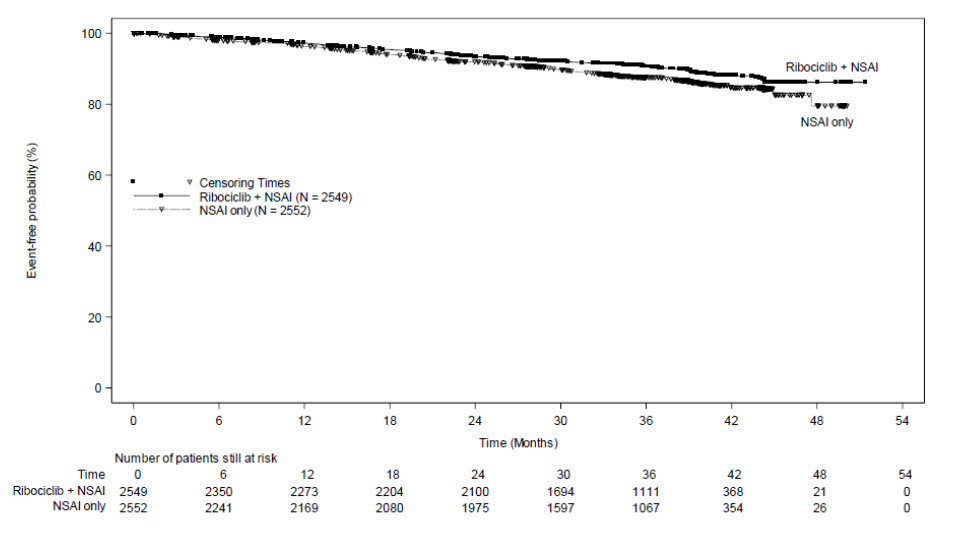 DRUG LABEL: KISQALI
NDC: 0078-0860 | Form: TABLET, FILM COATED
Manufacturer: Novartis Pharmaceuticals Corporation
Category: prescription | Type: HUMAN PRESCRIPTION DRUG LABEL
Date: 20251215

ACTIVE INGREDIENTS: RIBOCICLIB SUCCINATE 200 mg/1 1
INACTIVE INGREDIENTS: SILICON DIOXIDE; CROSPOVIDONE; HYDROXYPROPYL CELLULOSE, UNSPECIFIED; MAGNESIUM STEARATE; MICROCRYSTALLINE CELLULOSE; FERROSOFERRIC OXIDE; FERRIC OXIDE RED; LECITHIN, SOYBEAN; POLYVINYL ALCOHOL, UNSPECIFIED; TALC; TITANIUM DIOXIDE; XANTHAN GUM

HIGHLIGHTS OF PRESCRIBING INFORMATION

These highlights do not include all the information needed to use KISQALI safely and effectively. See full prescribing information for KISQALI.
KISQALI® (ribociclib) tablets, for oral use
Initial U.S. Approval: 2017

RECENT MAJOR CHANGES

Indications and Usage (1.1, 1.2) | 09/2024
Dosage and Administration (2.1, 2.2) | 09/2024
Warnings and Precautions (5.1, 5.3, 5.5, 5.6) | 09/2024

1 INDICATIONS AND USAGE

KISQALI is a kinase inhibitor indicated:

- in combination with an aromatase inhibitor for the adjuvant treatment of adults with hormone receptor (HR)-positive, human epidermal growth factor receptor 2 (HER2)-negative stage II and III early breast cancer at high risk of recurrence. (1)
- for the treatment of adults with HR-positive, HER2-negative advanced or metastatic breast cancer in combination with:
  - an aromatase inhibitor as initial endocrine-based therapy; or
  - fulvestrant as initial endocrine-based therapy or following disease progression on endocrine therapy. (1)

2 DOSAGE AND ADMINISTRATION

KISQALI tablets are taken orally with or without food in combination with an aromatase inhibitor or fulvestrant. (2)

Early Breast Cancer

- Recommended starting dose: 400 mg orally (two 200 mg tablets) taken once daily with or without food for 21 consecutive days followed by 7 days off treatment. (2.1)

Advanced or Metastatic Breast Cancer

- Recommended starting dose: 600 mg orally (three 200 mg tablets) taken once daily with or without food for 21 consecutive days followed by 7 days off treatment. (2.1)

Dose interruption, reduction, and/or discontinuation may be required based on individual safety and tolerability. (2.2)

3 DOSAGE FORMS AND STRENGTHS

- Tablets: 200 mg (3)

4 CONTRAINDICATIONS

None. (4)

5 WARNINGS AND PRECAUTIONS

- Interstitial Lung Disease (ILD)/Pneumonitis: Patients treated with CDK 4/6 inhibitors should be monitored for pulmonary symptoms indicative of ILD/pneumonitis. Interrupt and evaluate patients with new or worsening respiratory symptoms suspected to be due to ILD/pneumonitis. Permanently discontinue KISQALI in patients with recurrent symptomatic or severe ILD/pneumonitis. (2.2, 5.1)
- Severe Cutaneous Adverse Reactions (SCARs): Stevens-Johnson syndrome (SJS), toxic epidermal necrolysis (TEN), and drug-reaction with eosinophilia and systemic symptoms (DRESS) can occur with KISQALI treatment. Permanently discontinue KISQALI in patients with SCARs or other life-threatening cutaneous reactions. (2.2, 5.2)
- QT Interval Prolongation: Monitor electrocardiograms (ECGs) and electrolytes prior to initiation of treatment with KISQALI. Repeat ECGs at approximately Day 14 of the first cycle, and as clinically indicated. Monitor electrolytes at the beginning of each cycle for 6 cycles, and as clinically indicated. Avoid using KISQALI with drugs known to prolong QT interval and/or strong CYP3A inhibitors. (2.2, 5.3, 7.1, 7.4)
- Increased QT Prolongation with Concomitant Use of Tamoxifen: KISQALI is not indicated for concomitant use with tamoxifen. (5.4)
- Hepatotoxicity: Increases in serum transaminase and bilirubin levels have been observed. Perform liver function tests (LFTs) before initiating treatment with KISQALI. Monitor LFTs every 2 weeks for the first 2 cycles, at the beginning of each subsequent 4 cycles, and as clinically indicated. (2.2, 5.5)
- Neutropenia: Perform complete blood count (CBC) before initiating therapy with KISQALI. Monitor CBC every 2 weeks for the first 2 cycles, at the beginning of each subsequent 4 cycles, and as clinically indicated. (2.2, 5.6)
- Embryo-Fetal Toxicity: Can cause fetal harm. Advise females of reproductive potential of potential risk to a fetus and to use effective contraception during therapy. (5.7, 8.1, 8.3)

6 ADVERSE REACTIONS

- In patients with early breast cancer, the most common (incidence ≥ 20%) adverse reactions, including laboratory abnormalities, are lymphocytes decreased, leukocytes decreased, neutrophils decreased, hemoglobin decreased, alanine aminotransferase increased, aspartate aminotransferase increased, infections, creatinine increased, platelets decreased, headache, nausea, and fatigue. (6)
- In patients with advanced or metastatic breast cancer, the most common (incidence ≥ 20%) adverse reactions, including laboratory abnormalities, are leukocytes decreased, neutrophils decreased, hemoglobin decreased, lymphocytes decreased, aspartate aminotransferase increased, gamma glutamyl transferase increased, alanine aminotransferase increased, infections, nausea, creatinine increased, fatigue, platelets decreased, diarrhea, vomiting, headache, constipation, alopecia, cough, rash, back pain, and glucose serum decreased. (6)

To report SUSPECTED ADVERSE REACTIONS, contact Novartis Pharmaceuticals Corporation at 1-888-669-6682 or FDA at 1-800-FDA-1088 or www.fda.gov/medwatch.

7 DRUG INTERACTIONS

- CYP3A Inhibitors: Avoid concomitant use of KISQALI with strong CYP3A inhibitors. If strong inhibitors cannot be avoided, reduce KISQALI dose. (2.2, 7.1)
- CYP3A4 Inducers: Avoid concomitant use of KISQALI with strong CYP3A inducers. (7.2)
- CYP3A Substrates: The dose of CYP3A substrates may need to be reduced when given concurrently with KISQALI. (7.3)
- Drugs Known to Prolong QT Interval: Avoid concomitant use of drugs known to prolong QT interval, such as anti-arrhythmic medicines. (7.4)

8 USE IN SPECIFIC POPULATIONS

Lactation: Advise not to breastfeed. (8.2)

FULL PRESCRIBING INFORMATION

1 INDICATIONS AND USAGE

1.1 Early Breast Cancer

KISQALI is indicated in combination with an aromatase inhibitor for the adjuvant treatment of adults with hormone receptor (HR)-positive, human epidermal growth factor receptor 2 (HER2)-negative stage II and III early breast cancer at high risk of recurrence.

1.2 Advanced or Metastatic Breast Cancer

KISQALI is indicated for the treatment of adults with HR-positive, HER2-negative advanced or metastatic breast cancer in combination with:

- an aromatase inhibitor as initial endocrine-based therapy; or
- fulvestrant as initial endocrine-based therapy or following disease progression on endocrine therapy.

2 DOSAGE AND ADMINISTRATION

2.1 Recommended Dosage

Important Administration Instructions

KISQALI can be taken with or without food [see Clinical Pharmacology (12.3)].

Pre/perimenopausal women, or men, treated with the combination KISQALI plus an aromatase inhibitor or fulvestrant, should be treated with a luteinizing hormone-releasing hormone (LHRH) agonist according to current clinical practice standards.

Patients should take their dose of KISQALI at approximately the same time each day, preferably in the morning.

If the patient vomits after taking the dose, or misses a dose, no additional dose should be taken that day. The next prescribed dose should be taken at the usual time. KISQALI tablets should be swallowed whole (tablets should not be chewed, crushed or split prior to swallowing). No tablet should be ingested if it is broken, cracked, or otherwise not intact.

Early Breast Cancer

The recommended dosage of KISQALI is 400 mg (two 200 mg film-coated tablets) taken orally, once daily for 21 consecutive days followed by 7 days off in 28-day treatment cycles. KISQALI should be given in combination with an aromatase inhibitor. Refer to the Full Prescribing Information for the recommended dosage of the aromatase inhibitor.

In patients with early breast cancer, treatment with KISQALI should continue for 3 years or until disease recurrence or unacceptable toxicity occurs.

Advanced or Metastatic Breast Cancer

The recommended dosage of KISQALI is 600 mg (three 200 mg film-coated tablets) taken orally, once daily for 21 consecutive days followed by 7 days off in 28-day treatment cycles. KISQALI should be given in combination with endocrine therapy (fulvestrant or an aromatase inhibitor). Refer to the Full Prescribing Information for the recommended dose of endocrine therapy.

2.2 Dose Modifications

Dose Modifications for Adverse Reactions

The recommended dose modifications for adverse reactions are listed in Table 1.

Table 1: Recommended Dose Modification for Adverse Reactions
Level | KISQALI
 | Dose | Number of tablets
Early breast cancer
Starting dose | 400 mg/day | two 200 mg tablets
Dose reduction | 200 mg/day* | one 200 mg tablet
Advanced or metastatic breast cancer
Starting dose | 600 mg/day | three 200 mg tablets
First dose reduction | 400 mg/day | two 200 mg tablets
Second dose reduction | 200 mg/day* | one 200 mg tablet
*If dose reduction below 200 mg/day is required, discontinue KISQALI.

Tables 2, 3, 4, 5, 6, and 7 summarize recommendations for dose interruption, reduction, or discontinuation of KISQALI in the management of specific adverse reactions. Dose modification of KISQALI is recommended based on individual patient safety and tolerability.

Table 2: Dose Modification and Management for Interstitial Lung Disease/Pneumonitis
 | Grade 1 (asymptomatic) | Grade 2 (symptomatic) | Grade 3 (severe symptomatic) or 4 (life-threatening)
ILD/Pneumonitis [see Warnings and Precautions (5.1)] | No dose interruption or adjustment is required. Initiate appropriate medical therapy and monitor as clinically indicated. | Dose interruption until recovery to Grade ≤ 1 then consider resuming KISQALI at the next lower dose level*. If Grade 2 recurs, discontinue KISQALI. | Discontinue KISQALI.
Abbreviation: ILD, interstitial lung disease.
Grading according to Common Terminology Criteria for Adverse Events (CTCAE) version 4.03.
*An individualized benefit-risk assessment should be performed when considering resuming KISQALI.

Table 3: Dose Modification and Management for Cutaneous Adverse Reactions, Including SCARs
 | Grade 1 (< 10% body surface area (BSA) with active skin toxicity, no signs of systemic involvement) | Grade 2 (10%-30% BSA with active skin toxicity, no signs of systemic involvement) | Grade 3 (severe rash not responsive to medical management; > 30% BSA with active skin toxicity, signs of systemic involvement present; SJS*) | Grade 4 (any % BSA associated with extensive superinfection, with IV antibiotics indicated; life threatening consequences; TEN**)
Cutaneous adverse reactions, including SCARs [see Warnings and Precautions (5.2)] | No dose adjustment is required. Initiate appropriate medical therapy and monitor as clinically indicated. |  | Interrupt KISQALI until the etiology of the reaction has been determined. If the etiology is a SCAR, permanently discontinue KISQALI. If the etiology is not a SCAR, interrupt dose until recovery to Grade ≤ 1, then resume KISQALI at same dose level. If the cutaneous adverse reaction still recurs at Grade 3, resume KISQALI at the next lower dose level. | Permanently discontinue KISQALI.
Abbreviations: BSA, body surface area; SCARs, severe cutaneous adverse reactions; SJS, Stevens-Johnson syndrome; TEN, toxic epidermal necrolysis.
*SJS (Grade 3 and 4) is defined as skin sloughing covering < 10% BSA and 10%-30% BSA, respectively, with associated signs (e.g., erythema, purpura, epidermal detachment, and mucous membrane detachment).
**TEN (Grade 4) is defined as skin sloughing covering ≥ 30% BSA with associated symptoms (e.g., erythema, purpura, epidermal detachment, and mucous membrane detachment).
Grading according to Common Terminology Criteria for Adverse Events (CTCAE) version 4.03.

Table 4: Dose Modification and Management for QT Prolongation
QTcF* prolongation | Early breast cancer | Advanced or metastatic breast cancer
> 480 ms and ≤ 500 ms | Interrupt KISQALI treatment and wait until QTcF resolves to ≤ 480 ms
 | Resume at the same dose | Reduce to the next lower dose level
 | If QTcF > 480 ms recurs, interrupt KISQALI treatment and wait until QTcF resolves to ≤ 480 ms, then resume at next lower dose level.
> 500 ms | Interrupt KISQALI treatment and wait until QTcF resolves to ≤ 480 ms, then resume at next lower dose level. If QTcF > 500 ms recurs, discontinue KISQALI.
Permanently discontinue KISQALI if QTcF interval prolongation is either > 500 ms or > 60 ms change from baseline AND associated with any of the following: Torsades de Pointes, polymorphic ventricular tachycardia, syncope, or signs/symptoms of serious arrhythmia.
Note: If dose reduction below 200 mg/day is required, discontinue KISQALI.
Electrocardiograms (ECGs) should be assessed prior to initiation of treatment in all patients.
Repeat ECGs at approximately Day 14 of the first cycle, and as clinically indicated.
In case of QTcF prolongation at any given time during treatment, monitor ECG more frequently, and as clinically indicated
*QTcF = QT interval corrected by Fridericia’s formula.

Table 5: Dose Modification and Management for Hepatobiliary Toxicity
 | Grade 1 (> ULN – 3 x ULN) | Grade 2 (> 3 to 5 x ULN) | Grade 3 (> 5 to 20 x ULN) | Grade 4 (> 20 x ULN)
AST and/or ALT elevations from baseline*, WITHOUT increase in total bilirubin above 2 x ULN [see Warnings and Precautions (5.5)] | No dose adjustment is required. | Baseline* at < Grade 2: Dose interruption until recovery to ≤ baseline grade, then resume KISQALI at same dose level. If Grade 2 recurs, resume KISQALI at next lower dose level. ----------------------------- Baseline* at Grade 2: No dose interruption. | Dose interruption until recovery to ≤ baseline* grade, then resume at next lower dose level. If Grade 3 recurs, discontinue KISQALI. | Discontinue KISQALI.
Combined elevations in AST and/or ALT WITH total bilirubin increase, in the absence of cholestasis [see Warnings and Precautions (5.5)] | If patients develop ALT and/or AST > 3 x ULN along with total bilirubin > 2 x ULN irrespective of baseline grade, discontinue KISQALI.
Perform Liver Function Tests (LFTs) before initiating treatment with KISQALI.
Monitor LFTs every 2 weeks for the first 2 cycles, at the beginning of each subsequent 4 cycles, and as clinically indicated.
If Grade ≥ 2 abnormalities are noted, monitor more frequently, and as clinically indicated.
Abbreviations: AST, aspartate aminotransferase; ALT, alanine aminotransferase; ULN, upper limit of normal.
*Baseline = prior to treatment initiation.
Grading according to Common Terminology Criteria for Adverse Events (CTCAE) version 4.03.

Table 6: Dose Modification and Management for Neutropenia
 | Grade 1 or 2 (ANC 1000/mm^3 – < LLN) | Grade 3 (ANC 500 - < 1000/mm^3) | Grade 3 febrile* neutropenia | Grade 4 (ANC < 500/mm^3)
Neutropenia [see Warnings and Precautions (5.6)] | No dose adjustment is required. | Dose interruption until recovery to Grade ≤ 2. Resume KISQALI at the same dose level. If toxicity recurs at Grade 3, dose interruption until recovery, then resume KISQALI at the next lower dose level. | Dose interruption until recovery of neutropenia to Grade ≤ 2. Resume KISQALI at the next lower dose level. | Dose interruption until recovery to Grade ≤ 2. Resume KISQALI at the next lower dose level.
 | Perform complete blood counts (CBCs) before initiating treatment with KISQALI. Monitor CBC every 2 weeks for the first 2 cycles, at the beginning of each subsequent 4 cycles, and as clinically indicated.
Abbreviations: ANC, absolute neutrophil count; LLN, lower limit of normal.
*Grade 3 neutropenia with single episode of fever > 38.3°C (or) 38°C or above for more than one hour and/or concurrent infection.
Grading according to Common Terminology Criteria for Adverse Events (CTCAE) version 4.03.

Table 7: Dose Modification and Management for Other Toxicities*
 | Grade 1 or 2 | Grade 3 | Grade 4
Other Toxicities | No dose adjustment is required. Initiate appropriate medical therapy and monitor as clinically indicated. | Dose interruption until recovery to Grade ≤ 1 then resume KISQALI at same dose level. If Grade 3 recurs, resume KISQALI at the next lower dose level. | Discontinue KISQALI.
*Excluding interstitial lung disease (ILD)/pneumonitis, cutaneous adverse reactions, including severe cutaneous adverse reactions (SCARs), QT interval prolongation, hepatobiliary toxicity, and neutropenia.
Grading according to Common Terminology Criteria for Adverse Events (CTCAE) version 4.03.

Refer to the Full Prescribing Information for the coadministered aromatase inhibitor or fulvestrant for dose modification guidelines in the event of toxicity and other relevant safety information.

Dose Modification for Use with Strong CYP3A Inhibitors

Avoid concomitant use of KISQALI with strong CYP3A inhibitors and consider an alternative concomitant medication with less potential for CYP3A inhibition [see Drug Interactions (7.1)].

If a strong CYP3A inhibitor must be coadministered, reduce the KISQALI dose as shown in Table 8.

Table 8: Dose Modification for Use with Strong CYP3A Inhibitors
Indication | Co-administration with Strong CYP3A Inhibitors
Early breast cancer | Reduce the KISQALI dose to 200 mg once daily.
Advanced or metastatic breast cancer | Reduce the KISQALI dose to 400 mg once daily.

If the strong inhibitor is discontinued, change the KISQALI dose (after at least 5 half-lives of the strong CYP3A inhibitor) to the dose used prior to the initiation of the strong CYP3A inhibitor [see Drug Interactions (7.1), Clinical Pharmacology (12.3)].

Dose Modification for Hepatic Impairment

The recommended dose modifications for patients with hepatic impairment are shown in Table 9 [see Use in Specific Populations (8.6), Clinical Pharmacology (12.3)].

Table 9: Dose Modification for Hepatic Impairment
Indication | Mild hepatic impairment (Child-Pugh class A) | Moderate and severe hepatic impairment (Child-Pugh class B or C)
Early breast cancer | No dose adjustment is necessary | No dose adjustment is necessary
Advanced or metastatic breast cancer | No dose adjustment is necessary | KISQALI 400 mg once daily

Review the Full Prescribing Information for the co-administered aromatase inhibitor or fulvestrant for dose modifications related to hepatic impairment.

Dose Modification for Severe Renal Impairment

The recommended starting dose is 200 mg KISQALI once daily for patients with severe renal impairment [see Use in Specific Populations (8.7), Clinical Pharmacology (12.3)].

3 DOSAGE FORMS AND STRENGTHS

Tablet: 200 mg ribociclib (equivalent to 254.40 mg ribociclib succinate).

Film coated, light greyish violet, round, curved with beveled edges, debossed with “RIC” on one side and “NVR” on the other side.

4 CONTRAINDICATIONS

None.

5 WARNINGS AND PRECAUTIONS

5.1 Interstitial Lung Disease/Pneumonitis

Severe, life-threatening, or fatal interstitial lung disease (ILD) and/or pneumonitis can occur in patients treated with KISQALI and other CDK 4/6 inhibitors.

In patients with early breast cancer (NATALEE) who received 400 mg KISQALI plus a non-steroidal aromatase inhibitor (NSAI), 1.5% of patients had ILD/pneumonitis (Grade 1-2).

In patients with advanced or metastatic breast cancer (MONALEESA-2, MONALEESA-3, MONALEESA-7), 1.6% of patients had ILD/pneumonitis (any Grade, 0.4% had Grade 3-4, and 0.1% had a fatal outcome). Additional cases of ILD/pneumonitis have occurred in the postmarketing setting, some resulting in death [see Adverse Reactions (6.2)].

Monitor patients for pulmonary symptoms indicative of ILD/pneumonitis which may include hypoxia, cough, and dyspnea. In patients who have new or worsening respiratory symptoms suspected to be due to ILD or pneumonitis, interrupt KISQALI immediately and evaluate the patient. Permanently discontinue KISQALI in patients with severe ILD/pneumonitis or any recurrent symptomatic ILD/pneumonitis [see Dosage and Administration (2.2)].

5.2 Severe Cutaneous Adverse Reactions

Severe cutaneous adverse reactions (SCARs), including Stevens-Johnson syndrome (SJS), toxic epidermal necrolysis (TEN), and drug-induced hypersensitivity syndrome (DiHS)/drug reaction with eosinophilia and systemic symptoms (DRESS) can occur in patients treated with KISQALI [see Adverse Reactions (6.2)].

If signs or symptoms of severe cutaneous reactions occur, interrupt KISQALI until the etiology of the reaction has been determined [see Dosage and Administration (2.2)]. Early consultation with a dermatologist is recommended to ensure greater diagnostic accuracy and appropriate management.

If SJS, TEN, or DiHS/DRESS is confirmed, permanently discontinue KISQALI. Do not reintroduce KISQALI in patients who have experienced SCARs or other life-threatening cutaneous reactions during KISQALI treatment.

5.3 QT Interval Prolongation

KISQALI has been shown to prolong the QT interval in a concentration-dependent manner [see Clinical Pharmacology (12.2)].

Avoid KISQALI in patients who are at significant risk of developing Torsades de Pointes (TdP), including those with:

- congenital long QT syndrome;
- uncontrolled or significant cardiac disease, recent myocardial infarction, heart failure, unstable angina, bradyarrhythmias, uncontrolled hypertension, high degree atrioventricular block, severe aortic stenosis, or uncontrolled hypothyroidism;
- electrolyte abnormalities;
- taking drugs known to prolong QT interval and/or strong CYP3A inhibitors as this may lead to prolongation of the QTcF interval.

Based on the observed QT prolongation during treatment, KISQALI may require dose interruption, reduction or discontinuation as described in Table 4 [see Dosage and Administration (2.2), Drug Interactions (7.4)].

In patients with early breast cancer (NATALEE) who received 400 mg KISQALI plus NSAI, 8 out of 2494 patients (0.3%) had > 500 ms post-baseline QTcF interval value and 50 out of 2494 patients (2%) had > 60 ms QTcF increase from baseline. QTcF prolongation was reversible with dose interruption. The majority of QTcF prolongation occurred within the first four weeks of KISQALI. There were no reported cases of Torsades de Pointes.

In patients with advanced or metastatic breast cancer (MONALEESA-2, MONALEESA-3, and MONALEESA-7) who received 600 mg KISQALI plus NSAI or fulvestrant, 15 out of 1054 patients (1.4%) had a > 500 ms post-baseline QTcF value and 61 out of 1054 patients (6%) had a > 60 ms QTcF increase from baseline. QTcF prolongation was reversible with dose interruption. The majority of QTcF prolongation occurred within the first four weeks of KISQALI. There were no reported cases of Torsades de Pointes.

In MONALEESA-2, in the KISQALI plus letrozole treatment arm, there was one (0.3%) sudden death in a patient with Grade 3 hypokalemia and Grade 2 QT prolongation. No cases of sudden death were reported in MONALEESA-7 or MONALEESA-3 [see Adverse Reactions (6)].

Perform ECG in all patients prior to starting KISQALI. Initiate treatment with KISQALI only in patients with QTcF values less than 450 ms. Repeat ECG at approximately Day 14 of the first cycle, and as clinically indicated.

Monitor serum electrolytes (including potassium, calcium, phosphorous and magnesium) prior to the initiation of KISQALI at the beginning of the first 6 cycles, and as clinically indicated. Correct any abnormality before starting KISQALI [see Dosage and Administration (2.2)].

5.4 Increased QT Prolongation with Concomitant Use of Tamoxifen

Avoid use of tamoxifen with KISQALI. In MONALEESA-7, the observed mean QTcF increase from baseline was > 10 ms higher in the tamoxifen plus placebo subgroup compared with the non-steroidal aromatase inhibitors (NSAIs) plus placebo subgroup. In the placebo arm, an increase of > 60 ms from baseline occurred in 6/90 (7%) of patients receiving tamoxifen, and in no patients receiving an NSAI. An increase of > 60 ms from baseline in the QTcF interval was observed in 14/87 (16%) of patients in the KISQALI and tamoxifen combination and in 18/245 (7%) of patients receiving KISQALI plus an NSAI [see Clinical Pharmacology (12.2)].

5.5 Hepatotoxicity

In patients with early and advanced or metastatic breast cancer, drug-induced liver injury and increases in transaminases occurred with KISQALI.

In patients with early breast cancer (NATALEE) treated with KISQALI, drug-induced liver injury was reported in 9 patients (0.4%), of which 5 were Grade ≥ 3, and 8 had resolved as of the data cutoff. There were 8 (0.3%) clinically confirmed Hy’s Law cases (including 4 out of 9 drug-induced liver injury mentioned above), 6 of which had resolved within 303 days and 2 of which were improving, all after discontinuation of KISQALI. Grade 3 or 4 increases in alanine aminotransferase (ALT) and aspartate aminotransferase (AST) occurred in 8% and 4.7% respectively; including Grade 4 increases in ALT (1.5%) and AST (0.8%).

In patients with advanced or metastatic breast cancer (MONALEESA-2, MONALEESA-7 and MONALEESA-3) treated with KISQALI Grade 3 or 4 increases in ALT and AST occurred in 11% and 8%, respectively. Among the patients who had Grade ≥ 3 ALT/AST elevation, the median time-to-onset was 92 days for the KISQALI plus aromatase inhibitor or fulvestrant treatment arms. The median time to resolution to Grade ≤ 2 was 21 days in the KISQALI plus aromatase inhibitor or fulvestrant treatment arms. In MONALEESA-2 and MONALEESA-3, concurrent elevations in ALT or AST greater than three times the ULN and total bilirubin greater than two times the ULN, with normal alkaline phosphatase, in the absence of cholestasis (Hy’s Law) occurred in 6 (1%) patients and all patients recovered after discontinuation of KISQALI.

Perform liver function tests (LFTs) in all patients before initiating KISQALI. Monitor LFTs every 2 weeks for first 2 cycles, at the beginning of each of the subsequent 4 cycles, and as clinically indicated [see Dosage and Administration (2.2)].

Based on the severity of the transaminase elevations, KISQALI may require dose interruption, reduction, or discontinuation as described in Table 5 (Dose Modification and Management for Hepatobiliary Toxicity) [see Dosage and Administration (2.2)].

5.6 Neutropenia

KISQALI causes concentration-dependent neutropenia.

In patients with early breast cancer (NATALEE) who received KISQALI plus NSAI, 94%, including 45% of Grade 3 or 4, had a decrease in neutrophil counts (based on laboratory findings), 63% had an adverse reaction of neutropenia, and 0.3% had febrile neutropenia. The median time to Grade ≥ 2 neutropenia was 18 days. The median time to resolution of Grade ≥ 3 neutropenia to Grade < 3 was 10 days. Treatment discontinuation due to neutropenia was required in 1.1% of patients.

In patients with advanced or metastatic breast cancer (MONALEESA-2, MONALEESA-7, and MONALEESA-3) who received KISQALI plus NSAI or fulvestrant, 75% had neutropenia, 62% had Grade 3 or 4 decrease in neutrophil count (based on laboratory findings), and 1.7% had febrile neutropenia. The median time to Grade ≥ 2 neutropenia was 17 days. The median time to resolution of Grade ≥ 3 neutropenia to Grade < 3 was 12 days. Treatment discontinuation due to neutropenia was required in 1% of patients.

Perform a complete blood count (CBC) in all patients before initiating KISQALI. Monitor CBC every 2 weeks for the first 2 cycles, at the beginning of each subsequent 4 cycles, and as clinically indicated.

Based on the severity of the neutropenia, KISQALI may require dose interruption, reduction, or discontinuation as described in Table 6 [see Dosage and Administration (2.2)].

5.7 Embryo-Fetal Toxicity

Based on findings from animal studies and the mechanism of action, KISQALI can cause fetal harm when administered to a pregnant woman. In animal reproduction studies, administration of ribociclib to pregnant rats and rabbits during organogenesis caused embryo-fetal toxicities at maternal exposures that were 0.6 and 1.5 times the human clinical exposure, respectively, based on area under the curve (AUC). Advise pregnant women of the potential risk to a fetus. Advise women of reproductive potential to use effective contraception during therapy with KISQALI and for at least 3 weeks after the last dose [see Use in Specific Populations (8.1, 8.3), Clinical Pharmacology (12.1)].

6 ADVERSE REACTIONS

The following adverse reactions are discussed in greater detail in other sections of the labeling:

- Interstitial Lung Disease/Pneumonitis [see Warnings and Precautions (5.1)]
- Severe Cutaneous Adverse Reactions [see Warnings and Precautions (5.2)]
- QT Interval Prolongation [see Warnings and Precautions (5.3, 5.4)]
- Hepatotoxicity [see Warnings and Precautions (5.5)]
- Neutropenia [see Warnings and Precautions (5.6)]

6.1 Clinical Trials Experience

Because clinical trials are conducted under widely varying conditions, adverse reaction rates observed in the clinical trials of a drug cannot be directly compared to rates in the clinical trials of another drug and may not reflect the rates observed in practice.

The data described in WARNINGS AND PRECAUTIONS reflect exposure to KISQALI plus non-steroidal aromatase inhibitor (NSAI) in 2526 patients with early breast cancer (NATALEE), of whom 51% completed 36 months of KISQALI treatment. The most common (≥ 20%) adverse reactions, including laboratory abnormalities, were lymphocytes decreased (97%), leukocytes decreased (95%), neutrophils decreased (94%), hemoglobin decreased (47%), alanine aminotransferase increased (45%), aspartate aminotransferase increased (44%), infections (37%), creatinine increased (33%), platelets decreased (28%), headache (23%), nausea (23%), and fatigue (22%).

In addition, the pooled safety population described in the WARNINGS AND PRECAUTIONS reflects exposure to KISQALI in 1065 patients with advanced or metastatic breast cancer (MONALEESA-2, MONALEESA-3, MONALEESA-7), of whom 76% were exposed for 6 months or longer, and 62% were exposed for greater than one year. The most common (≥ 20%) adverse reactions, including laboratory abnormalities, were leukocytes decreased (95%), neutrophils decreased (93%), hemoglobin decreased (68%), lymphocytes decreased (66%), aspartate aminotransferase increased (55%), gamma-glutamyl transferase increased (53%), alanine aminotransferase increased (52%), infections (47%), nausea (47%), creatinine increased (42%), fatigue (35%), platelets decreased (34%), diarrhea (33%), vomiting (29%), headache (27%), constipation (25%), alopecia (25%), cough (24%), rash (24%), back pain (24%), and glucose serum decreased (20%).

NATALEE: KISQALI in Combination with a Non-steroidal Aromatase Inhibitor as Adjuvant Treatment

Adults with HR-positive, HER2-negative Stage II and III Early Breast Cancer at High Risk of Recurrence

The safety of KISQALI was evaluated in NATALEE, a clinical trial of 5101 patients who received KISQALI plus NSAI or NSAI alone, with or without goserelin [see Clinical Studies (14)]. The median duration of exposure to KISQALI was 33 months.

Serious adverse reactions occurred in 14% of patients who received KISQALI. Serious adverse reactions in > 0.5% of patients who received KISQALI included COVID-19 (1.1%), pneumonia (0.8%), and pulmonary embolism (0.6%).

Fatal adverse reactions occurred in 0.6% of patients who received KISQALI. Fatal adverse reactions in ≥ 0.1% of patients receiving KISQALI included COVID-19 or COVID-19 pneumonia (0.2%) and pulmonary embolism (0.1%).

Permanent discontinuation of KISQALI due to an adverse reaction occurred in 20% of patients. Adverse reactions which resulted in permanent discontinuation of KISQALI in ≥ 2% of patients were alanine aminotransferase or aspartate aminotransferase increased (8%).

Dosage interruptions of both KISQALI plus NSAI due to an adverse reaction occurred in 73% of patients. Adverse reactions which required dosage interruption in ≥ 5% of patients included neutropenia or neutrophil count decreased (43%), alanine aminotransferase or aspartate aminotransferase increased (11%), COVID-19 (10%), and hypomagnesemia (5%).

Dose reductions of KISQALI due to an adverse reaction occurred in 23% of patients. Adverse reactions which required dose reductions in ≥ 2% of patients included neutropenia or neutrophil count decreased (14%) and liver function abnormal (2.3%).

The most common (≥ 20% on KISQALI plus NSAI and ≥ 2% higher than placebo) adverse reactions, including laboratory abnormalities, were neutropenia, infections, nausea, headache, fatigue, leukopenia, and abnormal liver function tests.

Table 10 summarizes the adverse reactions in NATALEE.

Table 10: Adverse Reactions (≥ 10% and ≥ 2% Higher Than NSAI Alone Arm) in NATALEE
Adverse reaction | KISQALI + NSAI (n = 2526) |  | NSAI (n = 2441)
 | All Grades (%) | Grade 3 or 4 (%) | All Grades (%) | Grade 3 or 4 (%)
Infections and infestations
Infections^1 | 37 | 2.0 | 27 | 0.9
Nervous system disorders
Headache^2 | 23 | 0.4 | 17 | 0.2
Gastrointestinal disorders
Nausea^2 | 23 | 0.2 | 8 | 0.1
Diarrhea^2 | 15 | 0.6 | 6 | 0.1
Constipation^2 | 13 | 0.2 | 5 | 0
Abdominal pain^2 | 11 | 0.5 | 7 | 0.4
General disorders and administration-site conditions
Fatigue^2 | 22 | 0.8 | 13 | 0.2
Asthenia^2 | 17 | 0.6 | 12 | 0.1
Pyrexia^2 | 11 | 0.2 | 6 | 0.1
Skin and subcutaneous tissue disorders
Alopecia | 15 | 0 | 4.6 | 0
Respiratory, thoracic, and mediastinal disorders
Cough^2 | 13 | 0.1 | 8 | 0.1
Grading according to Common Terminology Criteria for Adverse Events (CTCAE) version 4.03.
^1Infections: urinary tract infections; respiratory tract infections.
^2Only includes a Grade 3 adverse reaction.

Clinically relevant adverse reactions reported in < 10% of patients who received KISQALI plus NSAI included rash (9%), dizziness (9%), vomiting (8%), peripheral edema (7%), pruritis (7%), dyspnea (7%), stomatitis (6%), oropharyngeal pain (6%), hypocalcemia (5%), hypokalemia (4.8%), decreased appetite (4.8%).

Table 11 summarizes the laboratory abnormalities in NATALEE.

Table 11: Select Laboratory Abnormalities (≥ 10%) in Patients in NATALEE Who Received KISQALI Plus NSAI
Laboratory abnormality | KISQALI + NSAI (n = 2526) |  | NSAI (n = 2441)
 | All Grades (%) | Grade 3 or 4 (%) | All Grades (%) | Grade 3 or 4 (%)
Hematology
Lymphocytes decreased | 97 | 19 | 88 | 6
Leukocytes decreased | 95 | 27 | 45 | 0.6
Neutrophils decreased | 94 | 45 | 35 | 1.7
Hemoglobin decreased | 47 | 0.6 | 26 | 0.3
Platelets decreased | 28 | 0.4 | 13 | 0.3
Chemistry
Alanine aminotransferase increased | 45 | 8 | 35 | 1
Aspartate aminotransferase increased | 44 | 5 | 33 | 1
Creatinine increased | 33 | 0.3 | 11 | 0

MONALEESA-2: KISQALI in Combination with Letrozole

Postmenopausal Women with HR-positive, HER2-negative Advanced or Metastatic Breast Cancer for Initial Endocrine-Based Therapy

The safety of KISQALI was evaluated in MONALEESA-2, a clinical trial of 668 postmenopausal women receiving KISQALI plus letrozole or placebo plus letrozole [see Clinical Studies (14)]. The median duration of exposure to KISQALI plus letrozole was 13 months with 58% of patients exposed for ≥ 12 months.

Serious adverse reactions occurred in 21% of patients who received KISQALI plus letrozole. Serious adverse reactions in ≥1 % of patients receiving KISQALI plus letrozole included abdominal pain (1.5%), vomiting (1.5%), constipation (1.2%), nausea (1.2%), anemia (1.2%), febrile neutropenia (1.2%), dyspnea (1.2%), and alanine aminotransferase increased (1.2%).

Fatal adverse reactions occurred in 1.8% of patients who received KISQALI. Fatal adverse reactions in ≥ 0.1% of patients receiving KISQALI included acute respiratory failure (0.6%), acute myocardial infarction, sudden death (with Grade 3 hypokalemia and Grade 2 QT prolongation), unknown cause, and pneumonia (0.3% each). Permanent discontinuation of both KISQALI and letrozole due to an adverse reaction occurred in 7% of patients. Permanent discontinuation of KISQALI alone occurred in 7% of patients. Adverse reactions which resulted in permanent discontinuation of both KISQALI and letrozole in ≥ 2% of patients were alanine aminotransferase increased (5%), aspartate aminotransferase increased (3%), and vomiting (2%).

Dosage interruptions of both KISQALI and letrozole due to an adverse reaction occurred in 71% of patients. Adverse reactions which required dosage interruption in ≥ 5% of patients included neutropenia (39%), neutrophils decreased (12%), vomiting (6%), nausea (5%), alanine aminotransferase increased (5%), and leukocytes decreased (5%).

Dose reductions of KISQALI due to an adverse reaction occurred in 45% of patients receiving KISQALI plus letrozole. Adverse reactions which required dose reductions in ≥ 2% of patients included neutropenia (24%), neutrophils decreased (8%), and alanine aminotransferase increased (3%).

Antiemetics and antidiarrheal medications were used to manage symptoms as clinically indicated.

The most common (≥ 20% on the KISQALI arm and ≥ 2% higher than placebo) adverse reactions, including laboratory abnormalities, were neutrophils decreased, leukocytes decreased, hemoglobin decreased, nausea, lymphocytes decreased, alanine aminotransferase increased, aspartate aminotransferase increased, fatigue, diarrhea, alopecia, vomiting, platelets decreased, constipation, headache, and back pain.

Table 12 summarizes the adverse reactions in MONALEESA-2.

Table 12: Adverse Reactions (≥ 10% and ≥ 2% Higher Than Placebo Arm) in MONALEESA-2
Adverse reaction | KISQALI + Letrozole (n = 334) |  | Placebo + Letrozole (n = 330)
 | All Grades (%) | Grade 3 or 4 (%) | All Grades (%) | Grade 3 or 4 (%)
Gastrointestinal disorders
Nausea^1 | 52 | 2.4 | 29 | 0.6
Diarrhea^1 | 35 | 1.2 | 22 | 0.9
Vomiting^1 | 29 | 3.6 | 16 | 0.9
Constipation^1 | 25 | 1.2 | 19 | 0
Stomatitis^1 | 12 | 0.3 | 7 | 0
Abdominal pain^1 | 11 | 1.2 | 8 | 0
General disorders and administration-site conditions
Fatigue | 37 | 2.4 | 30 | 0.9
Pyrexia^1 | 13 | 0.3 | 6 | 0
Peripheral edema^1 | 12 | 0 | 10 | 0
Skin and subcutaneous tissue disorders
Alopecia^1 | 33 | 0 | 16 | 0
Rash^1 | 17 | 0.6 | 8 | 0
Pruritus^1 | 14 | 0.6 | 6 | 0
Nervous system disorders
Headache^1 | 22 | 0.3 | 19 | 0.3
Insomnia^1 | 12 | 0.3 | 9 | 0
Musculoskeletal and connective tissue disorders
Back pain^1 | 20 | 2.1 | 18 | 0.3
Metabolism and nutrition disorders
Decreased appetite^1 | 19 | 1.5 | 15 | 0.3
Respiratory, thoracic and mediastinal disorders
Dyspnea^1 | 12 | 1.2 | 9 | 0.6
Infections and infestations
Urinary tract infections^1 | 11 | 0.6 | 8 | 0
Grading according to Common Terminology Criteria for Adverse Events (CTCAE) version 4.03.
^1Only includes a Grade 3 adverse reaction.

Clinically relevant adverse reactions in < 10% of patients in MONALEESA-2 receiving KISQALI plus letrozole included interstitial lung disease (0.3%), lung infiltration (0.3%), pneumonitis (0.3%), and pulmonary fibrosis (0.6%). Table 13 summarizes the laboratory abnormalities in MONALEESA-2.

Table 13: Select Laboratory Abnormalities (≥ 10%) in Patients in MONALEESA-2 Who Received KISQALI Plus Letrozole
Laboratory abnormality | KISQALI + Letrozole (n = 334) |  | Placebo + Letrozole (n = 330)
 | All Grades (%) | Grade 3 or 4 (%) | All Grades (%) | Grade 3 or 4 (%)
Hematology
Leukocytes decreased | 93 | 34 | 29 | 1.5
Neutrophils decreased | 93 | 60 | 24 | 1.2
Hemoglobin decreased | 57 | 1.8 | 26 | 1.2
Lymphocytes decreased | 51 | 14 | 22 | 3.9
Platelets decreased | 29 | 0.9 | 6 | 0.3
Chemistry
Alanine aminotransferase increased | 46 | 10 | 36 | 1.2
Aspartate aminotransferase increased | 44 | 7 | 32 | 1.5
Creatinine increased | 20 | 0.6 | 6 | 0
Phosphorous decreased | 13 | 5 | 4 | 0.6
Potassium decreased | 11 | 1.2 | 7 | 1.2

MONALEESA-7: KISQALI in Combination with a Non-Steroidal Aromatase Inhibitor

Pre/perimenopausal Patients with HR-positive, HER2-negative Advanced or Metastatic Breast Cancer for Initial Endocrine-Based Therapy

The safety of KISQALI was evaluated in MONALEESA-7, a clinical trial of 672 pre/perimenopausal patients with HR-positive, HER2-negative advanced or metastatic breast cancer receiving either KISQALI plus a NSAI or tamoxifen plus goserelin or placebo plus NSAI or tamoxifen plus goserelin [see Clinical Studies (14)]. The median duration of exposure in the KISQALI plus a NSAI arm was 15.2 months with 66% of patients exposed for ≥ 12 months. The safety data reported below are based on 495 pre/perimenopausal patients receiving KISQALI plus NSAI plus goserelin or placebo plus NSAI plus goserelin.

Serious adverse reactions occurred in 17% of patients who received KISQALI plus NSAI plus goserelin. Serious adverse reactions in ≥ 1% of patients receiving KISQALI plus NSAI plus goserelin included drug-induced liver injury (1.6%), abdominal pain (1.2%), dyspnea (1.2%), febrile neutropenia (1.2%), and back pain (1.2%).

Permanent discontinuation of both KISQALI and NSAI due to an adverse reaction occurred in 3% of patients. Permanent discontinuation of KISQALI alone occurred in 3% of patients. Adverse reactions which resulted in permanent discontinuation of both KISQALI and NSAI in ≥ 2% of patients were alanine aminotransferase increased (2%), and aspartate aminotransferase increased (2%).

Dosage interruptions of KISQALI plus NSAI plus goserelin due to an adverse reaction occurred in 73% of patients. Adverse reactions which required dosage interruption in ≥ 5% of patients included neutropenia (41%), neutrophils decreased (26%), and leukocytes decreased (6%).

Dose reductions of KISQALI due to an adverse reaction occurred in 33% of patients receiving KISQALI plus NSAI plus goserelin. Adverse reactions which required dose reductions in ≥ 2 % of patients included neutropenia (17%), neutrophils decreased (5%), and alanine aminotransferase increased (2%).

The most common (≥ 20% on the KISQALI arm and ≥ 2% higher than placebo) adverse reactions, including laboratory abnormalities, were leukocytes decreased, neutrophils decreased, hemoglobin decreased, lymphocytes decreased, gamma-glutamyl transferase increased, aspartate aminotransferase increased, infections, arthralgia, alanine aminotransferase increased, nausea, platelets decreased, and alopecia.

Table 14 summarizes the adverse reactions in MONALEESA-7.

Table 14: Adverse Reactions Occurring in ≥ 10% and ≥ 2% Higher Than Placebo Arm in MONALEESA-7 (NSAI) (All Grades)
Adverse reaction | KISQALI + NSAI + Goserelin (n = 248) |  | Placebo + NSAI + Goserelin (n = 247)
 | All Grades (%) | Grade 3 or 4 (%) | All Grades (%) | Grade 3 or 4 (%)
Infections and infestations
Infections1;2 | 36 | 1.6 | 24 | 0.4
Musculoskeletal and connective tissue disorders
Arthralgia^2 | 34 | 0.8 | 29 | 1.2
Gastrointestinal disorders
Nausea^2 | 32 | 0 | 20 | 0
Constipation^2 | 16 | 0 | 12 | 0
Stomatitis^2 | 10 | 0 | 8 | 0.4
Skin and subcutaneous tissue disorders
Alopecia^2 | 21 | 0 | 13 | 0
Rash^2 | 17 | 0.4 | 9 | 0
Pruritus^2 | 11 | 0 | 4 | 0
General disorders and administration-site conditions
Pyrexia^2 | 17 | 0.8 | 7 | 0
Pain in extremity^2 | 10 | 0 | 8 | 1.2
Respiratory, thoracic and mediastinal disorders
Cough^2 | 15 | 0 | 10 | 0
Abbreviation: NSAI, non-steroidal aromatase inhibitor.
Grading according to Common Terminology Criteria for Adverse Events (CTCAE) version 4.03.
^1Infections: urinary tract infections; respiratory tract infections, gastroenteritis, sepsis (< 1%).
^2Only includes a Grade 3 adverse reactions.

Clinically relevant adverse reactions in < 10% of patients in MONALEESA-7 receiving KISQALI plus NSAI included thrombocytopenia (9%), dry skin (9%), oropharyngeal pain (7%), dyspepsia (5%), lacrimation increased (4%), dry eye (4%), vitiligo (3%), hypocalcemia, (2%), blood bilirubin increased (1%), syncope (0.4%), and pneumonitis (0.4%).

Table 15: Select Laboratory Abnormalities (≥ 10%) in Patients in MONALEESA-7 Who Received KISQALI Plus NSAI Plus Goserelin
Laboratory abnormality | KISQALI + NSAI + Goserelin (n = 248) |  | Placebo + NSAI + Goserelin (n = 247)
 | All Grades (%) | Grade 3 or 4 (%) | All Grades (%) | Grade 3 or 4 (%)
Hematology
Leukocytes decreased | 93 | 36 | 30 | 0.8
Neutrophils decreased | 92 | 63 | 27 | 2.4
Hemoglobin decreased | 84 | 2.4 | 51 | 0.4
Lymphocytes decreased | 55 | 14 | 18 | 2.8
Platelets decreased | 26 | 0.4 | 9 | 0.4
Chemistry
Gamma-glutamyl transferase increased | 42 | 7 | 42 | 9
Aspartate aminotransferase increased | 37 | 4.8 | 35 | 1.6
Alanine aminotransferase increased | 33 | 6 | 31 | 1.6
Phosphorous decreased | 14 | 1.6 | 11 | 0.8
Potassium decreased | 11 | 1.2 | 14 | 1.2
Glucose serum decreased | 10 | 0.4 | 10 | 0.4
Creatinine increased | 8 | 0 | 2 | 0

MONALEESA-3: KISQALI in Combination with Fulvestrant

Postmenopausal Patients with HR-positive, HER2-negative Advanced or Metastatic Breast Cancer for Initial Endocrine-Based Therapy or After Disease Progression on Endocrine Therapy

The safety of KISQALI was evaluated in MONALEESA-3, a clinical trial of 724 postmenopausal women receiving KISQALI plus fulvestrant or placebo plus fulvestrant [see Clinical Studies (14)]. The median duration of exposure to KISQALI plus fulvestrant was 15.8 months with 58% of patients exposed for ≥ 12 months.

Serious adverse reactions occurred in 29% of patients who received KISQALI plus fulvestrant. Serious adverse reactions in ≥ 1% of patients receiving KISQALI plus fulvestrant included pneumonia (1.9%), nausea (1.4%), vomiting (1.4%), anemia (1.2%), dyspnea (1.2%), neutropenia (1.2%). One case (0.2%) of fatal adverse reaction (pneumonia) occurred in patients who received KISQALI plus fulvestrant.

Fatal adverse reactions occurred in 1.2% of patients who received KISQALI. Fatal adverse reactions in ≥ 0.1% of patients receiving KISQALI included cardiac failure, ventricular arrhythmia, pneumonia, acute respiratory distress, pulmonary embolism, and hemorrhagic shock (0.2% each). Permanent discontinuation of both KISQALI and fulvestrant due to an adverse reaction occurred in 8% of patients. Permanent discontinuation of KISQALI alone occurred in 9% of patients. Adverse reactions which resulted in permanent discontinuation of both KISQALI and fulvestrant in ≥ 2% of patients were alanine aminotransferase increased (5%), and aspartate aminotransferase increased (3%).

Dosage interruptions of KISQALI plus fulvestrant due to an adverse reaction occurred in 72% of patients. Adverse reactions which required dosage interruption in ≥ 5% of patients included neutropenia (40%), neutrophils decreased (13%), alanine aminotransferase increased (8%), aspartate aminotransferase increased (8%), and leukocytes decreased (5%).

Dose reductions of KISQALI due to an adverse reaction occurred in 32% of patients receiving KISQALI plus fulvestrant. Adverse reactions which required dose reductions in ≥ 2% of patients included neutropenia (15%), and neutrophils decreased (3%).

The most common (≥ 20% on the KISQALI arm and ≥ 2% higher than placebo) adverse reactions, including laboratory abnormalities, were leukocytes decreased, neutrophils decreased, lymphocytes decreased, creatinine increased, hemoglobin decreased, gamma-glutamyl transferase increased, aspartate aminotransferase increased, nausea, alanine aminotransferase increased, infections, platelets decreased, diarrhea, vomiting, constipation, glucose serum decreased, cough, rash, and pruritus.

Table 16 summarizes the adverse reactions in MONALEESA-3.

Table 16: Adverse Reactions (≥ 10% and ≥ 2% Higher Than Placebo Arm) in MONALEESA-3
Adverse reaction | KISQALI + Fulvestrant (n = 483) |  | Placebo + Fulvestrant (n = 241)
 | All Grades (%) | Grade 3 or 4 (%) | All Grades (%) | Grade 3 or 4 (%)
Gastrointestinal disorders
Nausea^2 | 45 | 1.4 | 28 | 0.8
Diarrhea^2 | 29 | 0.6 | 20 | 0.8
Vomiting^2 | 27 | 1.4 | 13 | 0
Constipation^2 | 25 | 0.8 | 12 | 0
Abdominal pain^2 | 17 | 1.4 | 13 | 0.8
Infections and infestations
Infections1;2;3 | 42 | 4.6 | 30 | 1.7
Skin and subcutaneous tissue disorders
Rash^2 | 23 | 0.8 | 8 | 0
Pruritus^2 | 20 | 0.2 | 7 | 0
Alopecia^2 | 19 | 0 | 5 | 0
Respiratory, thoracic and mediastinal disorders
Cough^2 | 22 | 0 | 15 | 0
Dyspnea | 15 | 1.4 | 12 | 1.7
Metabolism and nutrition disorders
Decreased appetite^2 | 16 | 0.2 | 13 | 0
General disorders and administration-site conditions
Peripheral edema^2 | 15 | 0 | 7 | 0
Pyrexia^2 | 11 | 0.2 | 7 | 0
Nervous system disorders
Dizziness^2 | 13 | 0.2 | 8 | 0
Grading according to Common Terminology Criteria for Adverse Events (CTCAE) version 4.03.
^1Infections: urinary tract infections; respiratory tract infections; gastroenteritis; sepsis (1%).
^2Only include Grade 3 adverse reactions.
^3Includes the following fatal adverse reactions: pneumonia (n = 1).

Clinically relevant adverse reactions in < 10% of patients in MONALEESA-3 receiving KISQALI plus fulvestrant included thrombocytopenia (9%) dry skin (8%), dysgeusia (7%), dry mouth (5%), vertigo (5%), dry eye (5%), lacrimation increased (4%), erythema (4%), hypocalcemia (4%), blood bilirubin increased (1%), syncope (1%), interstitial lung disease (0.4%), pneumonitis (0.4%), hypersensitivity pneumonitis (0.2%), and acute respiratory distress syndrome (0.2%).

Table 17: Select Laboratory Abnormalities (≥ 10%) in Patients in MONALEESA-3 Who Received KISQALI Plus Fulvestrant
Laboratory abnormality | KISQALI + Fulvestrant (n = 483) |  | Placebo + Fulvestrant (n = 241)
 | All Grades (%) | Grade 3 or 4 (%) | All Grades (%) | Grade 3 or 4 (%)
Hematology
Leukocytes decreased | 95 | 26 | 26 | 0.4
Neutrophils decreased | 92 | 53 | 21 | 0.8
Lymphocytes decreased | 69 | 16 | 35 | 4.1
Hemoglobin decreased | 60 | 4.3 | 35 | 2.9
Platelets decreased | 33 | 1.9 | 11 | 0
Chemistry
Creatinine increased | 65 | 1 | 33 | 0.4
Gamma-glutamyl transferase increased | 52 | 8 | 49 | 10
Aspartate aminotransferase increased | 50 | 7 | 43 | 2.9
Alanine aminotransferase increased | 44 | 11 | 37 | 1.7
Glucose serum decreased | 23 | 0 | 18 | 0
Phosphorous decreased | 18 | 4.6 | 8 | 0.8
Albumin decreased | 12 | 0 | 8 | 0

COMPLEEMENT-1: KISQALI in Combination with Letrozole and Goserelin or Leuprolide

Men with HR-positive, HER2-negative Advanced Breast Cancer for Initial Endocrine-Based Therapy

The safety of KISQALI in combination with letrozole was evaluated in men (n = 39) in an open-label, multicenter clinical trial for the treatment of adult patients with HR-positive, HER2-negative, advanced breast cancer who received no prior hormonal therapy for advanced disease (COMPLEEMENT-1) [see Clinical Studies (14)].

The median duration of exposure to KISQALI was 20.8 months (range, 0.5 to 30.6 months).

Other adverse reactions occurring in men treated with KISQALI plus letrozole and goserelin or leuprolide were similar to those occurring in women treated with KISQALI plus endocrine therapy.

6.2 Postmarketing Experience

The following adverse events have been reported during post-approval use of KISQALI. Because these events are reported voluntarily from a population of uncertain size, it is not always possible to reliably estimate their frequency or establish a causal relationship to drug exposure.

Respiratory Disorders: Interstitial lung disease/pneumonitis

Skin and Subcutaneous Tissue Disorders: Stevens-Johnson syndrome (SJS), toxic epidermal necrolysis (TEN), drug-induced hypersensitivity syndrome (DiHS)/drug reaction with eosinophilia, and systemic symptoms (DRESS)

7 DRUG INTERACTIONS

7.1 Drugs That May Increase Ribociclib Plasma Concentrations

CYP3A4 Inhibitors

Coadministration of strong CYP3A inhibitors increases ribociclib exposure [see Clinical Pharmacology (12.3)]. Increased ribociclib concentrations may increase the incidence and severity of adverse reactions, including QTcF prolongation [see Warnings and Precautions (5.3)]. Avoid concomitant use of strong CYP3A inhibitors with KISQALI and consider alternative concomitant medications with less potential for CYP3A inhibition.

In patients with early breast cancer, if coadministration of KISQALI with a strong CYP3A inhibitor cannot be avoided, reduce the dose of KISQALI to 200 mg once daily. In patients with advanced or metastatic breast cancer, if coadministration of KISQALI with a strong CYP3A inhibitor cannot be avoided, reduce the dose of KISQALI to 400 mg once daily [see Dosage and Administration (2.2)].

7.2 Drugs That May Decrease Ribociclib Plasma Concentrations

CYP3A Inducers

Coadministration of strong CYP3A inducers decreases the plasma exposure of ribociclib [see Clinical Pharmacology (12.3)]. Avoid concomitant use of strong CYP3A inducers and consider an alternate concomitant medication with no or minimal potential to induce CYP3A.

7.3 Effect of KISQALI on Other Drugs

CYP3A Substrates

Coadministration of sensitive CYP3A4 substrates with multiple doses of KISQALI increases the substrate exposure [see Clinical Pharmacology (12.3)]. For CYP3A substrates where minimal increases in the concentration may increase CYP3A substrate adverse reactions, monitor for increased adverse reactions of the CYP3A substrate during treatment with KISQALI. The dose of the sensitive CYP3A substrate may need to be reduced as KISQALI can increase its exposure.

7.4 Drugs That Prolong the QT Interval

Avoid coadministration of KISQALI with products with a known potential to prolong QT interval, such as antiarrhythmic drugs and other drugs that are known to prolong the QT interval. If concomitant use cannot be avoided, monitor ECG when initiating, during concomitant use, and as clinically indicated [see Warnings and Precautions (5.3), Clinical Pharmacology (12.2)].

8 USE IN SPECIFIC POPULATIONS

8.1 Pregnancy

Risk Summary

Based on findings from animal studies and the mechanism of action, KISQALI can cause fetal harm when administered to a pregnant woman [see Clinical Pharmacology (12.1)].

There are no available human data informing the drug-associated risk. In animal reproduction studies, administration of ribociclib to pregnant animals during organogenesis resulted in increased incidences of post implantation loss and reduced fetal weights in rats and increased incidences of fetal abnormalities in rabbits at exposures 0.6 or 1.5 times the exposure in humans, respectively, at the highest recommended dose of 600 mg/day based on AUC (see Data). Advise pregnant women of the potential risk to a fetus.

The background risk of major birth defects and miscarriage for the indicated population is unknown. However, the background risk of major birth defects is 2%-4% and of miscarriage is 15%-20% of clinically recognized pregnancies in the U.S. general population.

Data

Animal Data

In embryo-fetal development studies in rats and rabbits, pregnant animals received oral doses of ribociclib up to 1000 mg/kg/day and 60 mg/kg/day, respectively, during the period of organogenesis.

In rats, 300 mg/kg/day resulted in reduced maternal body weight gain and reduced fetal weights accompanied by skeletal changes related to the lower fetal weights. There were no significant effects on embryo-fetal viability or fetal morphology at 50 or 300 mg/kg/day.

In rabbits at doses ≥ 30 mg/kg/day, there were adverse effects on embryo-fetal development, including increased incidences of fetal abnormalities (malformations and external, visceral, and skeletal variants) and fetal growth (lower fetal weights). These findings included reduced/small lung lobes, additional vessel on the descending aorta, additional vessel on the aortic arch, small eyes, diaphragmatic hernia, absent accessory lobe or (partly) fused lung lobes, reduced/small accessory lung lobe, extra/rudimentary 13th ribs, misshapen hyoid bone, bent hyoid bone alae, and reduced number of phalanges in the pollex. There was no evidence of increased incidence of embryo-fetal mortality. There was no maternal toxicity observed at 30 mg/kg/day.

At 300 mg/kg/day in rats and 30 mg/kg/day in rabbits, the maternal systemic exposures (AUC) were approximately 0.6 and 1.5 times, respectively, the exposure in patients at the highest recommended dose of 600 mg/day.

8.2 Lactation

Risk Summary

It is not known if ribociclib is present in human milk. There are no data on the effects of ribociclib on the breastfed infant or on milk production. Ribociclib and its metabolites readily passed into the milk of lactating rats. Because of the potential for serious adverse reactions in breastfed infants from KISQALI, advise lactating women not to breastfeed while taking KISQALI and for at least 3 weeks after the last dose.

Data

In lactating rats administered a single dose of 50 mg/kg, exposure to ribociclib was 3.56-fold higher in milk compared to maternal plasma.

8.3 Females and Males of Reproductive Potential

Based on animal studies and mechanism of action, KISQALI can cause fetal harm when administered to a pregnant woman [see Use in Specific Populations (8.1)].

Pregnancy Testing

Verify pregnancy status in females of reproductive potential prior to starting treatment with KISQALI.

Contraception

Females

Advise females of reproductive potential to use effective contraception (methods that result in less than 1% pregnancy rates) during treatment with KISQALI and for at least 3 weeks after the last dose.

Infertility

Males

Based on animal studies, KISQALI may impair fertility in males of reproductive potential [see Nonclinical Toxicology (13.1)].

8.4 Pediatric Use

The safety and efficacy of KISQALI in pediatric patients has not been established.

8.5 Geriatric Use

Of the 2549 adults with early breast cancer who received KISQALI in NATALEE, 407 patients (16%) were ≥ 65 years of age and 123 patients (2.4%) were ≥ 75 years of age. No overall differences in safety or effectiveness of KISQALI were observed between older and younger adults with early breast cancer.

Of 334 patients with advanced or metastatic breast cancer who received KISQALI in MONALEESA-2, 150 patients (45%) were ≥ 65 years of age and 35 patients (11%) were ≥ 75 years of age. Of 484 patients with advanced or metastatic breast cancer who received KISQALI in MONALEESA-3, 226 patients (47%) were ≥ 65 years of age and 65 patients (14%) were ≥ 75 years of age. Of 248 patients with advanced or metastatic breast cancer who received KISQALI in MONALEESA-7, no patients were ≥ 65 years of age. No overall differences in safety or effectiveness of KISQALI were observed between older and younger adults with advanced or metastatic breast cancer.

8.6 Hepatic Impairment

No dose adjustment is necessary in patients with breast cancer who have mild hepatic impairment (Child-Pugh class A) [see Clinical Pharmacology (12.3)]. A reduced starting dose of 400 mg is recommended in patients with advanced or metastatic breast cancer who have moderate (Child-Pugh class B) and severe hepatic impairment (Child-Pugh class C) [see Dosage and Administration (2.2)].

8.7 Renal Impairment

No dose adjustment is necessary in patients with breast cancer who have mild to moderate (30 mL/min to 89 mL/min/1.73 m^2 ≤ estimated glomerular filtration rate (eGFR)) renal impairment. A reduced starting dose of 200 mg is recommended in patients with breast cancer who have severe renal impairment [see Dosage and Administration (2.2), Clinical Pharmacology (12.3)].

11 DESCRIPTION

KISQALI (ribociclib) is a kinase inhibitor.

The chemical name of ribociclib succinate is: Butanedioic acid—7-cyclopentyl-N,N-dimethyl-2-{[5-(piperazin-1-yl) pyridin-2-yl]amino}-7H-pyrrolo[2,3-d]pyrimidine-6-carboxamide (1/1).

Ribociclib succinate is a light yellow to yellowish brown crystalline powder. The molecular formula for ribociclib succinate is C23H30N8O·C4H6O4 and the molecular weight is 552.64 g/mol (Free base: 434.55 g/mol).

The chemical structure of ribociclib is shown below:

KISQALI film-coated tablets are supplied for oral use and contain 200 mg of ribociclib free base (equivalent to 254.40 mg ribociclib succinate). The tablets also contain colloidal silicon dioxide, crospovidone, hydroxypropylcellulose, magnesium stearate and microcrystalline cellulose. The film-coating contains iron oxide black, iron oxide red, lecithin (soya), polyvinyl alcohol (partially hydrolysed), talc, titanium dioxide, and xanthan gum as inactive ingredients.

12 CLINICAL PHARMACOLOGY

12.1 Mechanism of Action

Ribociclib is an inhibitor of cyclin-dependent kinase (CDK) 4 and 6. These kinases are activated upon binding to D-cyclins and are downstream of signaling pathways which lead to cell cycle progression and cellular proliferation. The cyclin D-CDK4/6 complex regulates cell cycle progression through phosphorylation of the retinoblastoma protein (pRb).

In vitro, ribociclib decreased pRb phosphorylation, resulting in arrest in the G1 phase of the cell cycle and reduced proliferation in breast cancer-derived models. In vivo, treatment with single agent ribociclib in a rat xenograft model with human tumor cells led to decreased tumor volumes, which correlated with inhibition of pRb phosphorylation. In studies using patient-derived estrogen receptor positive breast cancer xenograft models, combination of ribociclib and antiestrogen (e.g., letrozole) therapies resulted in increased tumor growth inhibition compared to each drug alone. Additionally, the combination of ribociclib and fulvestrant resulted in tumor growth inhibition in an estrogen receptor positive breast cancer xenograft model.

12.2 Pharmacodynamics

The exposure-response relationship and time course of pharmacodynamic response for the safety and effectiveness of KISQALI have not been fully characterized in patients.

Cardiac Electrophysiology

A concentration-QT analysis of the data in patients with breast cancer treated with KISQALI at doses ranging from 50 to 1200 mg (0.083 to 2 times of the approved recommended high dose) suggested that ribociclib causes concentration-dependent increases in QTcF interval [see Warnings and Precautions (5.3, 5.4)].

In patients with early breast cancer, the estimated mean QTcF interval change from baseline for the KISQALI 400 mg in combination with non-steroidal aromatase inhibitor (NSAI) was 10.0 ms (90% CI: 8.0, 11.9) at the mean steady-state Cmax [see Warnings and Precautions (5.3, 5.4)].

In patients with advanced or metastatic breast cancer the estimated mean QTcF interval change from baseline for the KISQALI 600 mg in combination with aromatase inhibitors or fulvestrant was 22.0 ms (90% CI: 20.6, 23.4) and 23.7 ms (90% CI: 22.3, 25.1), respectively, and was 34.7 ms (90% CI: 31.6, 37.8) in combination with tamoxifen at the mean steady-state Cmax [see Warnings and Precautions (5.3, 5.4)].

12.3 Pharmacokinetics

Ribociclib exhibited over-proportional increases in exposure (Cmax and AUC) across the dose range of 50 mg to 1200 mg (0.083 to 2 times of the approved recommended high dose) following both single dose and repeated doses of KISQALI. Following repeated 600 mg once daily administration, steady-state was generally achieved after 8 days and ribociclib accumulated with a mean accumulation ratio of 2.5 (range, 0.97 to 6.4), and mean (coefficient of variation (CV%)) steady-state ribociclib Cmax was 1820 (62%) ng/mL and AUC was 23800 (66%) ng*h/mL.

Absorption

The Tmax following KISQALI administration was between 1 and 4 hours. The mean absolute bioavailability of ribociclib after a single oral dose of 600 mg was 65.8%.

Food Effect: Compared to the fasted state, oral administration of a single 600 mg dose of KISQALI tablet with a high-fat, high-calorie meal (approximately 800 to 1000 calories with ~50% calories from fat, ~35% calories from carbohydrates, and ~15% calories from protein) had no clinically meaningful differences in ribociclib Cmax or AUCinf.

Distribution

Ribociclib protein binding in vitro was approximately 70% and independent of concentration (10 to 10,000 ng/mL). The mean in vivo blood-to-plasma ratio was 1.04. The apparent volume of distribution at steady-state (Vss/F) was 1090 L.

Metabolism

Ribociclib undergoes extensive hepatic metabolism mainly via CYP3A4 in humans. Following oral administration of a single 600 mg dose of radio-labeled ribociclib to humans, the primary metabolic pathways for ribociclib involved oxidation (dealkylation, C and/or N-oxygenation, oxidation (-2H)) and combinations thereof. Ribociclib was the major circulating drug-derived entity in plasma (44%). The major circulating metabolites included metabolite M13 (CCI284, N-hydroxylation), M4 (LEQ803, N-demethylation), and M1 (secondary glucuronide), each representing an estimated 9%, 9%, and 8% of total radioactivity, and 22%, 20%, and 18% of ribociclib exposure. Clinical activity of ribociclib was due primarily to parent drug, with negligible contribution from circulating metabolites.

Ribociclib was extensively metabolized with unchanged drug accounting for 17% and 12% in feces and urine, respectively. Metabolite LEQ803 represented approximately 14% and 4% of the administered dose in feces and urine, respectively.

Elimination

The mean plasma effective half-life (CV%) was 32.0 hours (63%) and the mean apparent oral clearance (CL/F) was 25.5 L/hr (66%) at steady-state following 600 mg dose of KISQALI in patients with advanced cancer. The steady state mean CL/F was 38.4 L/hr following the 400 mg dose of KISQALI in patients with early breast cancer.

The mean apparent plasma terminal half-life of ribociclib ranged from 29.7 to 54.7 hours and mean CL/F of ribociclib ranged from 39.9 to 77.5 L/hr at 600 mg across studies in healthy adults.

Following a single oral dose of radio-labeled ribociclib in healthy adults, 92% of the total administered radioactive dose was recovered within 22 days; 69% in feces and 23% in urine.

Specific Populations

Patients with Hepatic Impairment

Compared to adults with normal hepatic function, mild (Child-Pugh class A) hepatic impairment had no effect on the exposure of ribociclib; while in adults with moderate (Child-Pugh class B) hepatic impairment, the mean ratio was 1.44 for Cmax and 1.28 for AUCinf; and in adults with severe (Child-Pugh class C) hepatic impairment, the mean ratio was 1.32 for Cmax and 1.29 for AUCinf.

Patients with Renal Impairment

In adults with severe renal impairment and end stage renal disease, ribociclib AUCinf increased 2.4-fold and 3.8-fold, and Cmax increased 2.1-fold and 2.7-fold relative to the exposure in adults with normal renal function.

Mild or moderate renal impairment had no effect on the exposure of ribociclib. A sub-group analysis of data from studies following oral administration of KISQALI in patients with advanced cancer or early breast cancer who have mild to moderate renal impairment, AUC and Cmax were comparable to those in patients with normal renal function, suggesting no clinically meaningful effect of mild or moderate renal impairment on ribociclib exposure.

Effect of Age, Weight, Gender, and Race

No clinically relevant effects of age, body weight, gender, or race on the systemic exposure of ribociclib were identified.

Drug Interaction Studies

Clinical Studies and Model-Informed Approaches

Drugs That Affect Ribociclib Plasma Concentrations

CYP3A Inhibitors: Following a single 400 mg dose of KISQALI with ritonavir (a strong CYP3A inhibitor), ritonavir (100 mg twice a day for 14 days) increased ribociclib Cmax and AUCinf by 1.7-fold and 3.2-fold, respectively, compared to ribociclib alone. Cmax and AUC for LEQ803 (a prominent metabolite of ribociclib, accounting for less than 10% of parent exposure) decreased by 96% and 98%, respectively. A moderate CYP3A4 inhibitor (erythromycin) is predicted to increase ribociclib steady-state Cmax and AUC by 1.1-fold and 1.2-fold, respectively, following KISQALI 400 mg once daily, and 1.1-fold and 1.1-fold, respectively, following KISQALI 600 mg once daily.

CYP3A Inducers: Following a single 600 mg dose of KISQALI with rifampicin (a strong CYP3A4 inducer) at 600 mg daily for 14 days, ribociclib Cmax decreased by 81% and AUCinf decreased by 89%, while LEQ803 Cmax increased 1.7-fold and AUCinf decreased by 27% compared to ribociclib alone. A moderate CYP3A inducer (efavirenz) is predicted to decrease ribociclib steady-state Cmax by 55% and AUC by 74%, following KISQALI 400 mg once daily, and by 52% and 71%, respectively, following KISQALI 600 mg once daily.

Drugs That are Affected by KISQALI

CYP3A4 and CYP1A2 Substrates: In a cocktail study with midazolam (sensitive CYP3A4 substrate) multiple doses of ribociclib (400 mg once daily for 8 days) increased midazolam Cmax by 2.1-fold and increased AUCinf by 3.8-fold compared to midazolam alone. Administration of KISQALI 600 mg once daily is predicted to increase midazolam Cmax and AUC by 2.4-fold and 5.2-fold, respectively. The effect of multiple doses of 400 mg ribociclib on caffeine (sensitive CYP1A2 substrate) was minimal, with Cmax decreased by 10% and AUCinf increased by 20%. Only weak inhibitory effects on CYP1A2 substrates are predicted at KISQALI 600 mg once daily dose.

Gastric pH-Elevating Agents: Coadministration of ribociclib with drugs that elevate the gastric pH is not predicted to alter ribociclib absorption.

Letrozole: Data from a clinical trial in patients with breast cancer indicated no drug interaction between ribociclib and letrozole following coadministration of the drugs.

Anastrozole: Data from a clinical trial in patients with breast cancer indicated no clinically relevant drug interaction between ribociclib and anastrozole following coadministration of the drugs.

Exemestane: Data from a clinical trial in patients with breast cancer indicated no clinically relevant drug interaction between ribociclib and exemestane following coadministration of the drugs.

Fulvestrant: Data from a clinical trial in patients with breast cancer indicated no clinically relevant effect of fulvestrant on ribociclib exposure following coadministration of the drugs.

Tamoxifen: KISQALI is not indicated for concomitant use with tamoxifen. Data from a clinical trial in patients with breast cancer indicated that tamoxifen Cmax and AUC increased approximately 2-fold following coadministration of KISQALI 600 mg.

In vitro Studies

Effect of Ribociclib on CYP Enzymes: In vitro, ribociclib was a reversible inhibitor of CYP1A2, CYP2E1 and CYP3A4/5 and a time-dependent inhibitor of CYP3A4/5, at clinically relevant concentrations. In vitro evaluations indicated that ribociclib has no potential to inhibit the activities of CYP2A6, CYP2B6, CYP2C8, CYP2C9, CYP2C19, and CYP2D6 at clinically relevant concentrations. It has no potential for time-dependent inhibition of CYP1A2, CYP2C9, and CYP2D6, and no induction of CYP1A2, CYP2B6, CYP2C9, and CYP3A4 at clinically relevant concentrations.

Effect of Ribociclib on Transporters: In vitro evaluations indicated that ribociclib has a low potential to inhibit the activities of drug transporters P-gp, OATP1B1/B3, OCT1, MATEK2 at clinically relevant concentrations. Ribociclib may inhibit BCRP, OCT2, MATE1, and human BSEP at clinically relevant concentrations.

Effect of Transporters on Ribociclib: Based on in vitro data, P-gp and BCRP mediated transport are unlikely to affect the extent of oral absorption of ribociclib at therapeutic doses. Ribociclib is not a substrate for hepatic uptake transporters OATP1B1/1B3 or OCT1 in vitro.

13 NONCLINICAL TOXICOLOGY

13.1 Carcinogenesis, Mutagenesis, Impairment of Fertility

In a 2-year carcinogenicity study with oral administration of ribociclib daily in cycles of 3 weeks on/1 week off, ribociclib was not carcinogenic at doses up to 50 mg/kg in male rats and 600 mg/kg in female rats. Systemic exposure in male and female rats were 1.3 and 1.8 times, respectively, the human exposure at the highest recommended dose of 600 mg/day based on AUC.

Ribociclib was not mutagenic in an in vitro bacterial reverse mutation (Ames) assay or clastogenic in an in vitro human lymphocyte chromosomal aberration assay or an in vivo rat bone marrow micronucleus assay.

In a fertility and early embryonic development study, female rats received oral doses of ribociclib for 14 days prior to mating through the first week of pregnancy. Ribociclib did not affect reproductive function, fertility or early embryonic development at doses up to 300 mg/kg/day (approximately 0.6 times the clinical exposure in patients at the highest recommended dose of 600 mg/day based on AUC).

A fertility study in male rats has not been performed with ribociclib. In repeat-dose toxicity studies with oral administration of ribociclib daily for 3 weeks on/1 week off in rats up to 26 weeks duration and dogs up to 39 weeks duration, atrophic changes in testes were reported. Findings included degeneration of seminiferous tubular epithelia in the testes and hypospermia and luminal cellular debris in the epididymides of rats and dogs and vacuolation of epithelia in the epididymides of rats. These findings were observed at doses ≥ 75 mg/kg in rats and ≥ 1 mg/kg in dogs which resulted in systemic exposures that were 1.4 and 0.03 times the human exposure at the highest recommended daily dose of 600 mg/day based on AUC, respectively. These effects can be linked to a direct anti-proliferative effect on the testicular germ cells resulting in atrophy of the seminiferous tubules and showed a trend towards reversibility in rats and dogs after a four-week non-dosing period.

13.2 Animal Toxicology and/or Pharmacology

In vivo cardiac safety studies in dogs demonstrated dose and concentration related QTc interval prolongation at an exposure similar to patients receiving the recommended dose of 600 mg. There is a potential to induce incidences of premature ventricular contractions (PVCs) at elevated exposures (approximately 5-fold the anticipated clinical Cmax).

14 CLINICAL STUDIES

14.1 Early Breast Cancer

NATALEE: KISQALI in Combination with a Non-steroidal Aromatase Inhibitor (NSAI) with or without Goserelin

Adults with HR-positive, HER2-negative Stage II and III Early Breast Cancer at High Risk of Recurrence

NATALEE (NCT03701334) was a randomized (1:1), open-label, multicenter study in adults (N = 5101) with HR-positive, HER2-negative early breast cancer that was:

- Anatomic Stage Group IIB-III, or
- Anatomic Stage Group IIA that is either:
  - Node positive or
  - Node negative, with:
    - Histologic Grade 3, or
    - Histologic Grade 2, with any of the following criteria:
      - Ki67 ≥ 20%
      - High risk by gene signature testing

Applying TNM criteria, NATALEE included patients with any lymph node involvement, or if no nodal involvement either tumor size > 5 cm, or tumor size 2 to 5 cm with either Grade 2 (and high genomic risk or Ki67 ≥ 20%) or Grade 3.

Participants were randomized to receive KISQALI 400 mg plus a non-steroidal aromatase inhibitor (NSAI, letrozole or anastrozole) or NSAI only, and goserelin as indicated. Randomization was stratified by Anatomic Stage, prior treatment (neoadjuvant versus adjuvant chemotherapy), menopausal status (premenopausal and males versus postmenopausal) and region (North America/Western Europe/Oceania versus rest of the world).

The main efficacy outcome measure was invasive disease-free survival (iDFS). iDFS was defined as the time from randomization to the first occurrence of: local invasive breast recurrence, regional invasive recurrence, distant recurrence, death (any cause), contralateral invasive breast cancer, or second primary non-breast invasive cancer (excluding basal and squamous cell carcinomas of the skin). Overall survival (OS) was an additional outcome measure.

KISQALI was given orally at a dose of 400 mg once daily for 21 consecutive days followed by 7 days off treatment in combination with letrozole 2.5 mg or anastrozole 1 mg orally once daily for 28 days; goserelin 3.6 mg was administered on Day 1 of each 28-day cycle. KISQALI was administered for up to 36 months in the absence of recurrence or unacceptable toxicity. NSAI was administered for at least 5 years.

The median age was 52 years (range, 24 to 90); > 99% women (n = 19 men); 73% White, 13% Asian, 1.7% Black or African American, < 0.1% Native Hawaiian or other Pacific Islander, < 0.1% American Indian or Alaskan Native; 8.5% Hispanic or Latino; 99% ECOG 0-1; 88% node positive disease; 88% received prior (neo)adjuvant chemotherapy.

A statistically significant improvement in iDFS was observed in the intent-to-treat (ITT) population at an interim analysis. The efficacy results at the time of the final iDFS analysis are summarized in Table 18 and Figure 1. At the time of the iDFS final analysis, OS was immature, and a total of 172 (3.5%) of patients had died across both study arms.

Table 18: Efficacy Results – NATALEE (Investigator Assessment, Intent-to-Treat Population)
 | KISQALI + NSAI +/- Goserelin | NSAI +/- Goserelin
Invasive Disease-Free Survival (iDFS)a | N = 2549 | N = 2552
Events (n, %) | 226 (8.9) | 283 (11.1)
Hazard ratio (95% CI) | 0.749 (0.628, 0.892)
iDFS at 36 months (%, 95% CI) | 90.7 (89.3, 91.8) | 87.6 (86.1, 88.9)
Abbreviations: CI, confidence interval; iDFS, invasive disease-free survival.
aiDFS was statistically significant at an interim analysis based on a one-sided stratified log-rank p-value of 0.0014.

Figure 1: Kaplan-Meier Plot of iDFS – NATALEE (Investigator Assessment, Intent-to-Treat Population)

14.2 Advanced or Metastatic Breast Cancer

MONALEESA-2: KISQALI in Combination with Letrozole

Postmenopausal Women with HR-positive, HER2-negative Advanced or Metastatic Breast Cancer for Initial Endocrine-Based Therapy

MONALEESA-2 (NCT01958021) was a randomized (1:1), double-blind, placebo-controlled, multicenter clinical study of KISQALI plus letrozole vs. placebo plus letrozole conducted in postmenopausal women (N = 668) with HR-positive, HER2-negative, advanced breast cancer who received no prior therapy for advanced disease.

Participants were randomized to receive either KISQALI plus letrozole or placebo plus letrozole, stratified according to the presence of liver and/or lung metastases. Letrozole 2.5 mg was given orally once daily for 28 days, with either KISQALI 600 mg or placebo orally once daily for 21 consecutive days followed by 7 days off until disease progression or unacceptable toxicity. The major efficacy outcome measure for the study was investigator-assessed progression-free survival (PFS) using Response Evaluation Criteria in Solid Tumors (RECIST) v1.1.

The median age was 62 years (range, 23 to 91) and 45% of patients were older than 65. The majority of patients were White (82%), and all patients had an ECOG performance status of 0 or 1. A total of 47% of patients had received chemotherapy and 51% had received antihormonal therapy in the neoadjuvant or adjuvant setting. Thirty-four percent (34%) of patients had de novo metastatic disease, 21% had bone only disease, and 59% had visceral disease.

The efficacy results are summarized in Table 19, Figure 2 and Figure 3. The PFS assessment based on a blinded independent central radiological review was consistent with investigator assessment. Consistent results were observed across patient subgroups of prior adjuvant or neoadjuvant chemotherapy or hormonal therapies, liver and/or lung involvement, and bone-only metastatic disease.

Table 19: Efficacy Results – MONALEESA-2 (Investigator Assessment, Intent-to-Treat Population)
 | KISQALI + Letrozole | Placebo + Letrozole
Progression-Free Survival | N = 334 | N = 334
Events (n, %) | 93 (27.8) | 150 (44.9)
Median (months, 95% CI) | NR (19.3 – NR) | 14.7 (13.0 – 16.5)
Hazard Ratio (95% CI) | 0.556 (0.429, 0.720)
p-value | < 0.0001a
Overall Survival | N = 334 | N = 334
Events (n, %) | 181 (54.2) | 219 (65.6)
Median (months, 95% CI) | 63.9 (52.4, 71.0) | 51.4 (47.2, 59.7)
Hazard Ratio (95% CI) | 0.765 (0.628, 0.932)
p-value | 0.004a
Overall Response Rate for patients with measurable disease | N = 256 | N = 245
Overall Response Rate (95% CI) | 52.7 (46.6, 58.9) | 37.1 (31.1, 43.2)
Abbreviations: CI, confidence interval; NR, not reached.
ap-value estimated from one-sided log-rank test.

Figure 2: Kaplan-Meier Plot of Progression-Free Survival – MONALEESA-2 (Investigator Assessment, Intent-to-Treat Population)

Figure 3: Kaplan-Meier Plot of Overall Survival – MONALEESA-2 (Investigator Assessment, Intent-to-Treat Population)

MONALEESA-7: KISQALI in Combination with a Non-Steroidal Aromatase Inhibitor with or without Goserelin

Pre/perimenopausal Patients with HR-positive, HER2-negative Advanced or Metastatic Breast Cancer for Initial Endocrine-Based Therapy

MONALEESA-7 (NCT02278120) was a randomized (1:1), double-blind, placebo-controlled study of KISQALI plus either a NSAI or tamoxifen and goserelin vs. placebo plus either a NSAI or tamoxifen and goserelin conducted in pre/perimenopausal women (N = 672) with HR-positive, HER2-negative, advanced breast cancer who received no prior endocrine therapy for advanced disease.

Participants were randomized to receive KISQALI plus NSAI or tamoxifen plus goserelin or placebo plus NSAI or tamoxifen plus goserelin, stratified according to the presence of liver and/or lung metastases, prior chemotherapy for advanced disease and endocrine combination partner (tamoxifen and goserelin vs. NSAI and goserelin). NSAI (letrozole 2.5 mg or anastrozole 1 mg) or tamoxifen 20 mg were given orally once daily on a continuous daily schedule, goserelin was administered as a sub-cutaneous injection on Day 1 of each 28-day cycle, with either KISQALI 600 mg or placebo orally once daily for 21 consecutive days followed by 7 days off until disease progression or unacceptable toxicity. The major efficacy outcome measure for the study was investigator-assessed progression-free survival (PFS) using Response Evaluation Criteria in Solid Tumors (RECIST) v1.1.

The median age was 44 years (range, 25 to 58). Patients were primarily White (58%), Asian (29%), or Black (3%). Nearly all patients (99%) had an ECOG performance status of 0 or 1. Of the 672 patients, 33% had received chemotherapy in the adjuvant vs. 18% in the neoadjuvant setting and 40% had received endocrine therapy in the adjuvant vs. 0.7% in the neoadjuvant setting prior to study entry. Forty percent (40%) of patients had de novo metastatic disease, 24% had bone only disease, and 57% had visceral disease. Demographics and baseline disease characteristics were balanced and comparable between study arms, and endocrine combination partner.

The efficacy results from a pre-specified subgroup analysis of 495 patients who had received KISQALI or placebo with NSAI plus goserelin are summarized in Table 20, Figure 4, and Figure 5. Consistent results were observed in stratification factor subgroups of disease site and prior chemotherapy for advanced disease.

Table 20: Efficacy Results – MONALEESA-7 (NSAI, Investigator Assessment)
 | KISQALI + NSAI + Goserelin | Placebo + NSAI + Goserelin
Progression-Free Survival^1 | N = 248 | N = 247
Events (n, %) | 92 (37.1) | 132 (53.4)
Median (months, 95% CI) | 27.5 (19.1, NR) | 13.8 (12.6, 17.4)
Hazard Ratio (95% CI) | 0.569 (0.436, 0.743)
Overall Survival | N = 248 | N = 247
Events (n, %) | 61 (24.6) | 80 (32.4)
Median (months, 95% CI) | NR (NR, NR) | 40.7 (37.4, NR)
Hazard Ratio (95% CI) | 0.699 (0.501, 0.976)
Overall Response Rate for patients with measurable disease*,1 | N = 192 | N = 199
Overall Response Rate (95% CI) | 50.5 (43.4, 57.6) | 36.2 (29.5, 42.9)
Abbreviations: CI, confidence interval; NR, not reached; NSAI, non-steroidal aromatase inhibitors.
*Based on confirmed responses.
^1Investigator Assessment.

Figure 4: Kaplan-Meier Plot of Progression-Free Survival – MONALEESA-7 (NSAI, Investigator Assessment)

Figure 5: Kaplan-Meier Plot of Overall Survival – MONALEESA-7 (NSAI, Investigator Assessment)

MONALEESA-3: KISQALI in Combination with Fulvestrant

Postmenopausal Women with HR-positive, HER2-negative Advanced or Metastatic Breast Cancer for Initial Endocrine-Based Therapy or After Disease Progression on Endocrine Therapy

MONALEESA-3 (NCT06129786) was a randomized (2:1) double-blind, placebo-controlled study of ribociclib in combination with fulvestrant for the treatment of postmenopausal women (N = 726) with hormone receptor positive, HER2-negative, advanced breast cancer who have received no or only one line of prior endocrine treatment.

Participants were randomized to receive KISQALI 600 mg and fulvestrant or placebo and fulvestrant, stratified according to the presence of liver and/or lung metastases and prior endocrine therapy for advanced or metastatic disease. Fulvestrant 500 mg was administered intramuscularly on Days 1, 15, 29, and once monthly thereafter, with either KISQALI 600 mg or placebo given orally once daily for 21 consecutive days followed by 7 days off until disease progression or unacceptable toxicity. The major efficacy outcome measure for the study was investigator-assessed progression-free survival (PFS) using Response Evaluation Criteria in Solid Tumors (RECIST) v1.1.

The median age was 63 years (range, 31 to 89). Of the patients enrolled, 47% were 65 years and older, including 14% age 75 years and older. The patients enrolled were primarily White (85%), Asian (9%), and Black (0.7%). Nearly all patients (99.7%) had an ECOG performance status of 0 or 1. Patients enrolled in this study were treated in the first- or second-line setting, and 19% had de novo metastatic disease. Forty-three percent (43%) of patients had received chemotherapy in the adjuvant vs. 13% in the neoadjuvant setting, and 59% had received endocrine therapy in the adjuvant vs. 1% in the neoadjuvant setting prior to study entry. Twenty-one percent (21%) of patients had bone only disease, and 61% had visceral disease. Demographics and baseline disease characteristics were balanced and comparable between study arms.

The efficacy results from MONALEESA-3 are summarized in Table 21, Figure 6, and Figure 7. Consistent results were observed in stratification factor subgroups of disease site and prior endocrine treatment for advanced disease.

Table 21: Efficacy Results – MONALEESA-3 (Investigator Assessment, Intent-to-Treat Population)
 | KISQALI + Fulvestrant | Placebo + Fulvestrant
Progression-Free Survivala,1 | N = 484 | N = 242
Events (n, %) | 210 (43.4) | 151 (62.4)
Median (months, 95% CI) | 20.5 (18.5, 23.5) | 12.8 (10.9, 16.3)
Hazard Ratio (95% CI) | 0.593 (0.480, 0.732)
p-valuea | < 0.0001
Overall Survival | N = 484 | N = 242
Events (n, %) | 167 (34.5) | 108 (44.6)
Median (months, 95% CI) | NR (42.5, NR) | 40.0 (37.0, NR)
Hazard Ratio (95% CI) | 0.724 (0.568, 0.924)
p-valuea | 0.00455
Overall Response Rate for patients with measurable disease*,1 | N = 379 | N = 181
Overall Response Rate (95% CI) | 40.9 (35.9, 45.8) | 28.7 (22.1, 35.3)
Abbreviations: CI, confidence interval; NR, not reached.
ap-value is obtained from the one-sided log-rank.
*Based on confirmed responses.
^1Investigator Assessment.

Figure 6: Kaplan-Meier Plot of Progression-Free Survival – MONALEESA-3 (Investigator Assessment, Intent-to-Treat Population)

Figure 7: Kaplan-Meier Plot of Overall Survival – MONALEESA-3 (Investigator Assessment, Intent-to-Treat Population)

COMPLEEMENT-1: KISQALI in combination with Letrozole with or without Goserelin or Leuprolide

Men with HR-positive, HER2-negative Advanced or Metastatic Breast Cancer for Initial Endocrine-Based Therapy

COMPLEEMENT-1 (NCT 02941926) was an open-label, multicenter clinical study of ribociclib in combination with letrozole and goserelin or leuprolide for the treatment of adults with HR-positive, HER2-negative, advanced breast cancer who received no prior hormonal therapy for advanced disease.

The study included 39 male patients who received KISQALI 600 mg orally once daily for 21 consecutive days followed by 7 days off; and letrozole 2.5 mg orally once daily for 28 days; and goserelin 3.6 mg as injectable subcutaneous implant or leuprolide 7.5 mg as intramuscular injection administered on Day 1 of each 28-day cycle. Patients were treated until disease progression or unacceptable toxicity occurred.

Male patients enrolled in this study had a median age of 62 years (range, 33 to 80). Of these patients, 39% were 65 years and older, including 10% aged 75 years and older. The male patients enrolled were White (72%), Asian (8%), and Black (3%), with 17% unknown. Nearly all male patients (97%) had an ECOG performance status of 0 or 1. The majority of male patients (97%) had 4 or less metastatic sites, which were primarily bone and visceral (69% each). Table 22 summarizes the efficacy results in male patients from COMPLEEMENT-1.

Table 22: Efficacy Results in Male Patients^1 – COMPLEEMENT-1 (Investigator Assessment, Intent-to-Treat Population)
 | KISQALI + Letrozole + Goserelin or Leuprolide
Overall Response Rate for patients with measurable disease*,2 | N = 32
Overall Response Rate (95% CI) | 46.9 (29.1, 65.3)
Duration of Response (DoR)^3 | N = 15
Median (months, 95% CI) | NR (21.3, NR)
Patients with DoR ≥ 12 months, n (%) | 12 (80.0)
Abbreviations: CI, confidence interval, NR, not reached.
*Based on confirmed responses.
^1Patients with measurable disease.
^2Investigator Assessment.
^3Proportion of patients with complete response or partial response.

16 HOW SUPPLIED/STORAGE AND HANDLING

KISQALI (ribociclib) Tablets

Each film-coated tablet contains 200 mg of ribociclib free base.

Light greyish violet, round, curved with beveled edge, debossed with “RIC” on one side and “NVR” on the other side; available in:

Carton of 3 blister packs (63 tablets total) – each blister pack contains a 7-day supply of 21 tablets (200 mg per tablet)
(600 mg daily dose). NDC 0078-0874-63

Carton of 3 blister packs (42 tablets total) – each blister pack contains a 7-day supply of 14 tablets (200 mg per tablet)
(400 mg daily dose). NDC 0078-0867-42

Carton of 1 blister pack (21 tablets total) – each blister pack contains a 21-day supply of 21 tablets (200 mg per tablet)
(200 mg daily dose). NDC 0078-0860-01

Store at room temperature at 20°C to 25°C (68°F to 77°F), excursions permitted between 15°C and 30°C (59°F and 86°F).

Store in the original blister package in order to protect from moisture.

17 PATIENT COUNSELING INFORMATION

Advise the patient to read the FDA-approved patient labeling (Patient Information).

Interstitial Lung Disease/Pneumonitis

Advise patients to immediately report new or worsening respiratory symptoms [see Warnings and Precautions (5.1)].

Severe Cutaneous Adverse Reactions

Inform patients of the signs and symptoms of severe cutaneous adverse reactions (e.g., skin pain/burning, rapidly-spreading skin rash, and/or mucosal lesions accompanied by fever or flu-like symptoms). Advise patients to contact their healthcare provider immediately if they develop signs and symptoms of severe cutaneous adverse reactions [see Warnings and Precautions (5.2)].

QT Prolongation

Inform patients of the signs and symptoms of QT prolongation. Advise patients to contact their healthcare provider immediately for signs or symptoms of QT prolongation [see Warnings and Precautions (5.3, 5.4)].

Hepatobiliary Toxicity

Inform patients of the signs and symptoms of hepatobiliary toxicity. Advise patients to contact their healthcare provider immediately for signs or symptoms of hepatobiliary toxicity [see Warnings and Precautions (5.5)].

Neutropenia

Advise patients of the possibility of developing neutropenia and to immediately contact their healthcare provider should they develop a fever, particularly in association with any suggestion of infection [see Warnings and Precautions (5.6)].

Embryo-Fetal Toxicity

- Advise pregnant women and females of reproductive potential of the potential risk to a fetus. Advise females to inform their healthcare provider of a known or suspected pregnancy [see Warnings and Precautions (5.7), Use in Specific Populations (8.1)].
- Advise females of reproductive potential to use effective contraception during KISQALI therapy and for at least 3 weeks after the last dose [Use in Specific Populations (8.3)].

Lactation

Advise lactating women not to breastfeed during treatment with KISQALI and for at least 3 weeks after the last dose [see Use in Specific Populations (8.2)].

Drug Interactions

- Inform patients to avoid strong CYP3A inhibitors, strong CYP3A inducers, and drugs known to prolong the QT interval [see Drug Interactions (7.1, 7.2, 7.4)].

Dosing

- Instruct patients to take the doses of KISQALI at approximately the same time every day and to swallow whole (do not chew, crush, or split them prior to swallowing) [see Dosage and Administration (2.1)].
- If patient vomits or misses a dose, advise the patient to take the next prescribed dose at the usual time [see Dosage and Administration (2.1)].
- Advise the patient that KISQALI may be taken with or without food [see Dosage and Administration (2.1)].

Distributed by:
Novartis Pharmaceuticals Corporation
East Hanover, New Jersey 07936

© Novartis

T2025-57

PATIENT INFORMATION
KISQALI® (kis kah' lee)
(ribociclib)
tablets

What is the most important information I should know about KISQALI?

KISQALI may cause serious side effects, including:

- Lung problems. KISQALI may cause severe or life-threatening inflammation of the lungs during treatment that may lead to death. Tell your healthcare provider right away if you have any new or worsening symptoms, including:
  - trouble breathing or shortness of breath
  - cough with or without mucus
  - chest pain
- Severe skin reactions. Tell your healthcare provider or get medical help right away if you get severe rash or rash that keeps getting worse, reddened skin, flu-like symptoms, skin pain or burning, blistering of the lips, eyes or mouth, blisters on the skin or skin peeling, with or without fever.
- Heart rhythm problems (QT prolongation). KISQALI can cause a heart problem known as QT prolongation This condition can cause an abnormal heartbeat and may lead to death.
  - Your healthcare provider should check your heart and do blood tests before and during treatment with KISQALI.
  - Tell your healthcare provider right away if you have a change in your heartbeat (a fast or irregular heartbeat), or if you feel dizzy or faint.
- Liver problems. KISQALI can cause serious liver problems. Your healthcare provider should do blood tests to check your liver before and during treatment with KISQALI. Tell your healthcare provider right away if you get any of the following signs and symptoms of liver problems:

o yellowing of your skin or the whites of your eyes (jaundice)
o dark or brown (tea-colored) urine
o feeling very tired

o loss of appetite
o pain on the upper right side of your stomach area (abdomen)
o bleeding or bruising more easily than normal

- Low white blood cell counts (neutropenia). Low white blood cell counts are very common during treatment with KISQALI and may result in infections that may be severe. Your healthcare provider should check your white blood cell counts before and during treatment with KISQALI. Tell your healthcare provider right away if you have signs and symptoms of low white blood cell counts or infections, such as fever and chills.

Your healthcare provider may tell you to decrease your dose, temporarily stop or completely stop taking KISQALI if you develop certain serious side effects during treatment with KISQALI.
See “What are the possible side effects of KISQALI?” for more information about side effects.

What is KISQALI?
KISQALI is a prescription medicine used to treat adults with hormone receptor (HR)-positive, human epidermal growth factor receptor 2 (HER2)-negative breast cancer:

- in combination with an aromatase inhibitor for stage II and III early breast cancer with a high risk of coming back.
- that has gotten worse or has spread to other parts of the body (advanced or metastatic breast cancer) in combination with:
  - an aromatase inhibitor as the first endocrine-based therapy, or
  - fulvestrant as the first endocrine-based therapy or following disease progression on endocrine therapy.

It is not known if KISQALI is safe and effective in children.

Before taking KISQALI, tell your healthcare provider about all of your medical conditions, including if you:

- have any heart problems, including heart failure, irregular heartbeats, and QT prolongation
- have ever had a heart attack
- have a slow heartbeat (bradycardia)
- have high blood pressure that is not controlled
- have decreased thyroid gland function (hypothyroidism)
- have problems with the amount of potassium, calcium, phosphorus, or magnesium in your blood
- have fever, chills, or any other signs or symptoms of infection
- have liver problems
- have kidney problems
- are pregnant, or plan to become pregnant. KISQALI can harm your unborn baby.
  - If you are able to become pregnant, your healthcare provider should do a pregnancy test before you start treatment with KISQALI.
  - Females who are able to become pregnant and who take KISQALI should use effective birth control during treatment and for at least 3 weeks after the last dose of KISQALI.
  - Talk to your healthcare provider about birth control methods that may be right for you during this time.
  - If you become pregnant or think you are pregnant, tell your healthcare provider right away.
- are breastfeeding or plan to breastfeed. It is not known if KISQALI passes into your breast milk. Do not breastfeed during treatment with KISQALI and for at least 3 weeks after the last dose of KISQALI.

Tell your healthcare provider about all the medicines you take, including prescription and over-the-counter medicines, vitamins, and herbal supplements. KISQALI and other medicines may affect each other causing side effects. Know the medicines you take. Keep a list of them to show your healthcare provider or pharmacist when you get a new medicine.

How should I take KISQALI?

- Take KISQALI exactly as your healthcare provider tells you.
- Do not change your dose or stop taking KISQALI without talking to your healthcare provider.
- Swallow KISQALI tablets whole. Do not chew, crush, or split KISQALI tablets before swallowing them.
- Take KISQALI each day at about the same time, preferably in the morning.
- Take KISQALI with or without food.
- Do not take any KISQALI tablets that are broken, cracked, or that look damaged.
- If you miss a dose of KISQALI or vomit after taking a dose of KISQALI, do not take another dose on that day. Take your next dose at your regular time.

What are the possible side effects of KISQALI?
KISQALI may cause serious side effects, including:

- See "What is the most important information I should know about KISQALI?"

The most common side effects of KISQALI in people with early breast cancer include:

• decreased white blood cell counts
• decreased red blood cell counts
• increased liver function tests
• infections
• increased kidney function test

• decreased platelet counts
• nausea
• headache
• tiredness

The most common side effects of KISQALI in people with advanced or metastatic breast cancer include:

• decreased white blood cell counts
• decreased red blood cell counts
• increased liver function tests
• infections

• nausea
• increased kidney function test
• tiredness
• decreased platelet counts

• diarrhea
• vomiting
• headache
• constipation
• hair loss

• cough
• rash
• back pain
• low blood sugar level

KISQALI may cause fertility problems in males, which may affect your ability to father a child. Talk to your healthcare provider if this is a problem for you.

Tell your healthcare provider if you have any side effect that bothers you or that does not go away.

These are not all of the possible side effects of KISQALI. For more information, ask your healthcare provider or pharmacist.

Call your doctor for medical advice about side effects. You may report side effects to FDA at 1-800-FDA-1088.

How should I store KISQALI?

- Store KISQALI at room temperature between 68°F to 77°F (20°C to 25°C).
- Store KISQALI in the original blister package in order to protect from moisture.

Keep KISQALI and all medicines out of the reach of children.

General information about the safe and effective use of KISQALI.

Medicines are sometimes prescribed for purposes other than those listed in a Patient Information leaflet. Do not use KISQALI for a condition for which it was not prescribed. Do not give KISQALI to other people, even if they have the same symptoms you have. It may harm them. You can ask your pharmacist or healthcare provider for more information about KISQALI that is written for health professionals.

What are the ingredients in KISQALI?

Active ingredient: ribociclib

Inactive ingredients: colloidal silicon dioxide, crospovidone, hydroxypropylcellulose, magnesium stearate, and microcrystalline cellulose. The film-coating contains iron oxide black, iron oxide red, lecithin (soya), polyvinyl alcohol (partially hydrolyzed), talc, titanium dioxide, and xanthan gum.

Distributed by: Novartis Pharmaceuticals Corporation, East Hanover, New Jersey 07936

© Novartis

For more information, go to www.KISQALI.com or call 1-888-669-6682.

This Patient Information has been approved by the U.S. Food and Drug Administration.

Revised: September 2025

T2025-58

PRINCIPAL DISPLAY PANEL

NDC 0078-0860-01

Rx only

Kisqali®
(ribociclib)
tablets

200 mg daily dose

(one 200 mg tablet)

21 Film-coated tablets

Contents: 1 individual monthly blister pack.
Blister pack contains 21 tablets (200 mg per tablet).

NOVARTIS

PRINCIPAL DISPLAY PANEL

NDC 0078-0867-42

Rx only

Kisqali®
(ribociclib)
tablets

400 mg daily dose

(two 200 mg tablets)

42 Film-coated tablets

Contents: 3 individual weekly blister packs.
Each blister pack contains 14 tablets (200 mg per tablet).

NOVARTIS

PRINCIPAL DISPLAY PANEL

NDC 0078-0874-63

Rx only

Kisqali®
(ribociclib)
tablets

600 mg daily dose

(three 200 mg tablets)

63 Film-coated tablets

Contents: 3 individual weekly blister packs.
Each blister pack contains 21 tablets (200 mg per tablet).

NOVARTIS